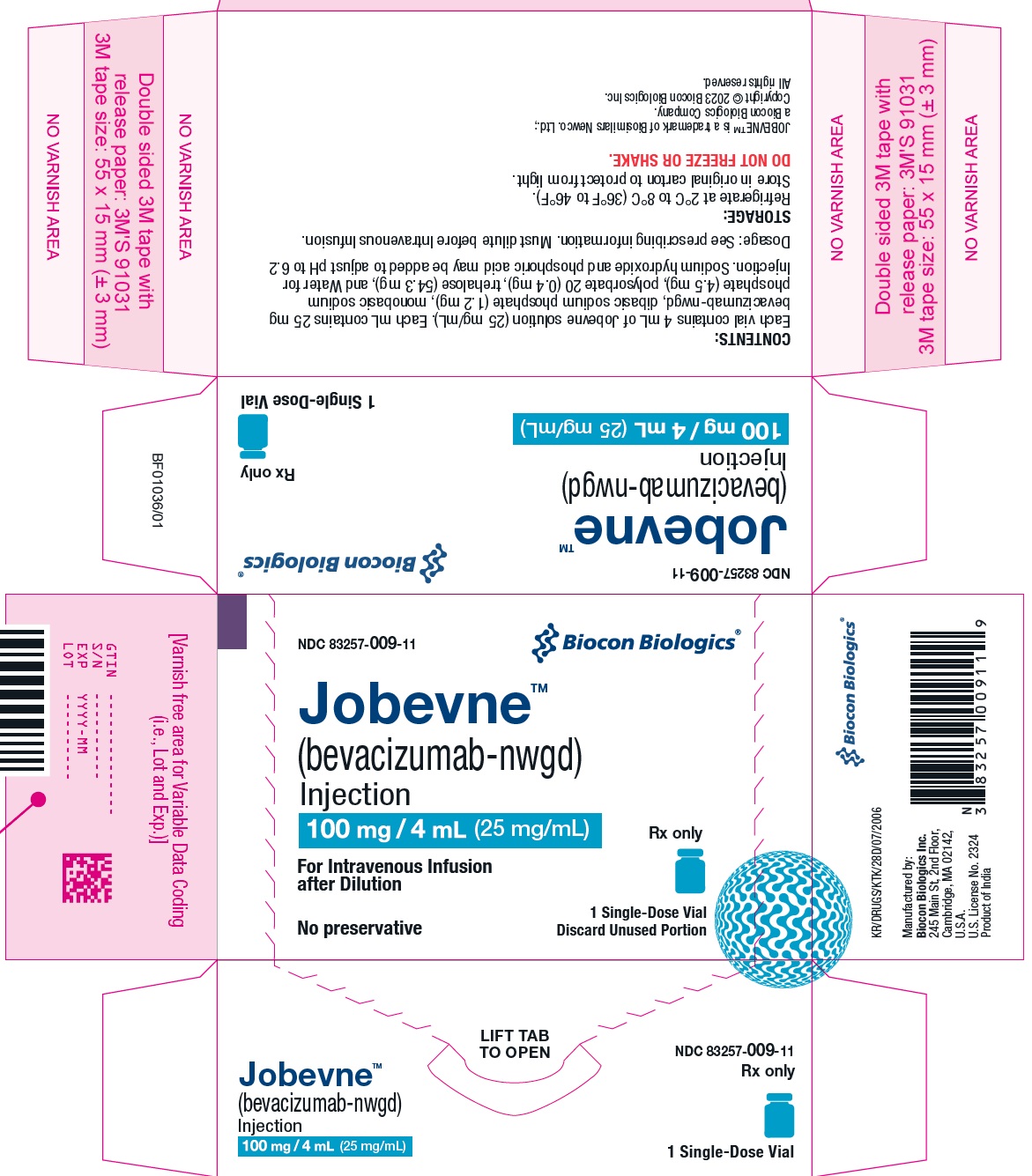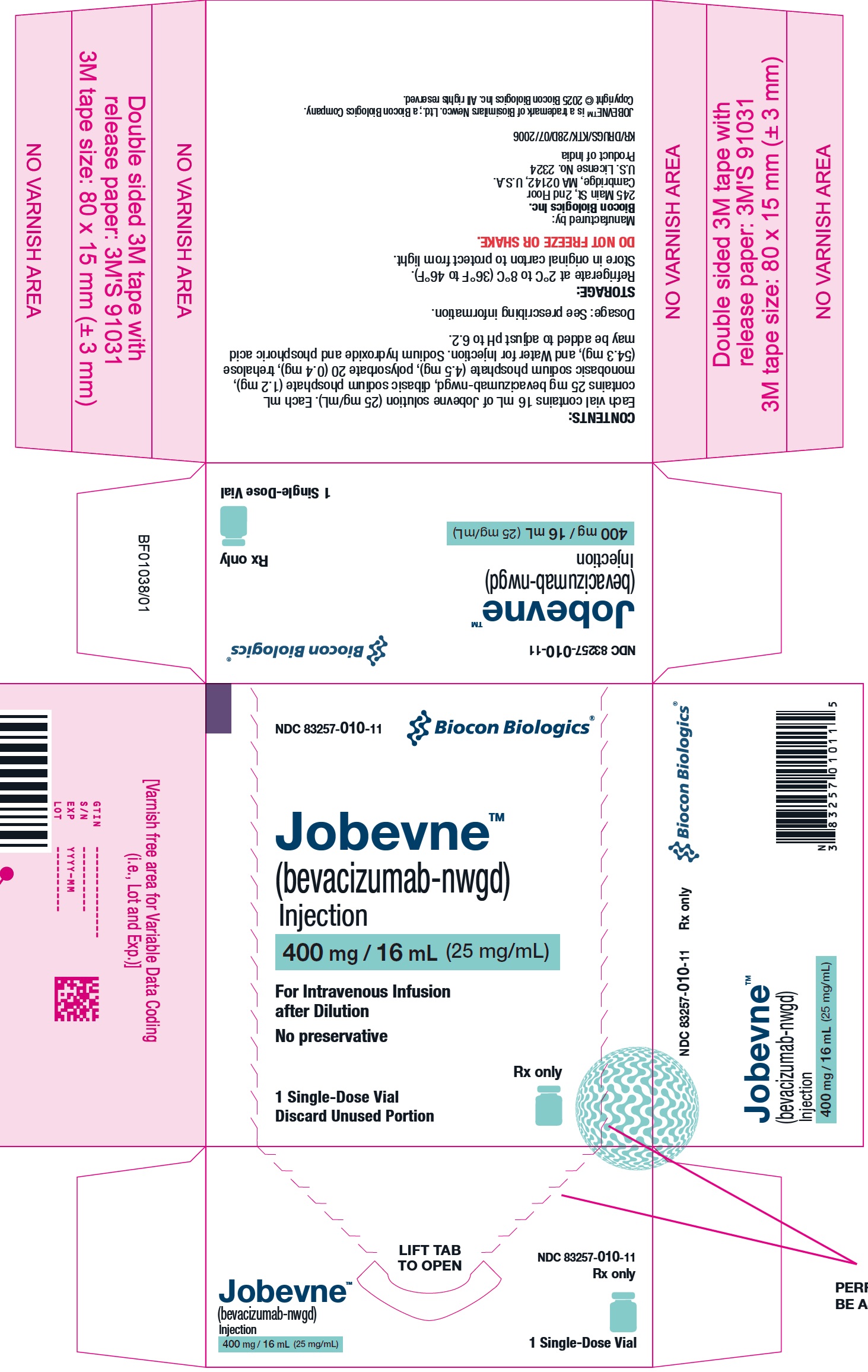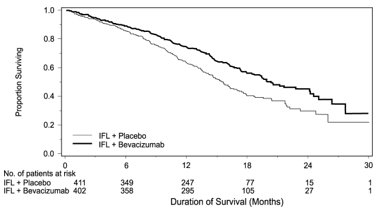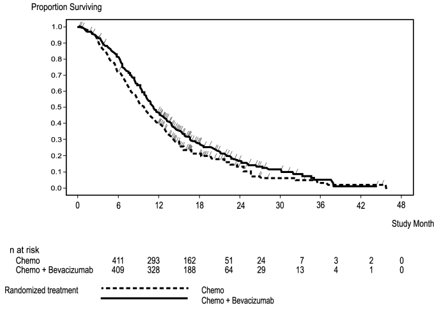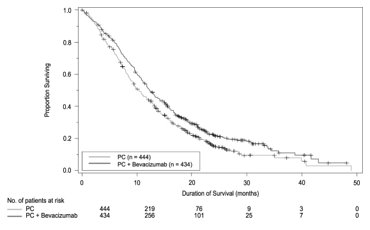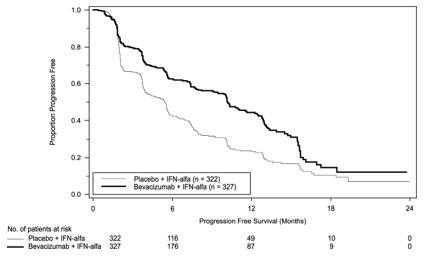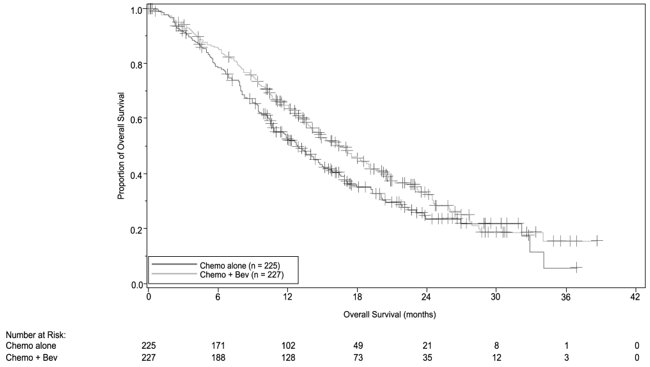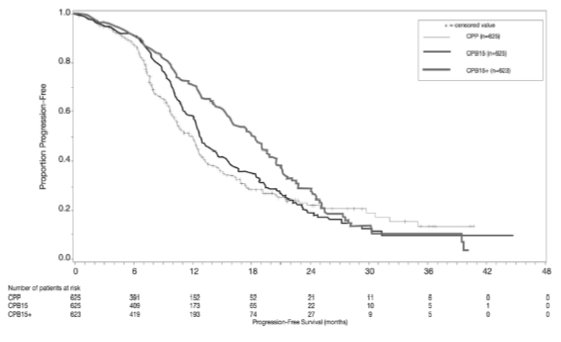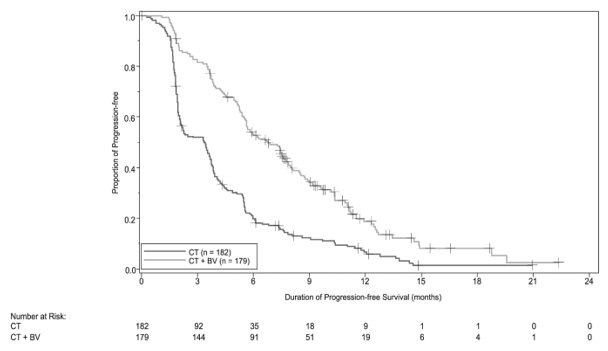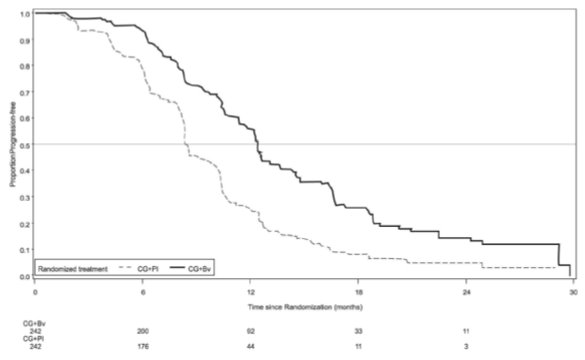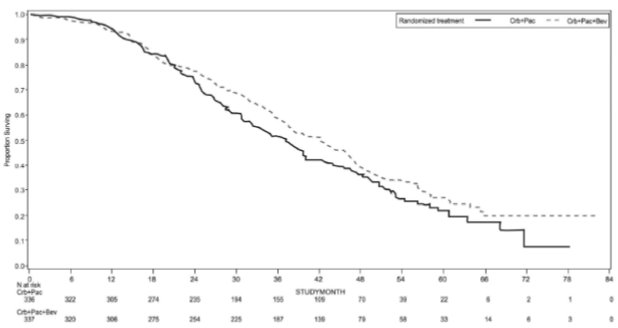 DRUG LABEL: JOBEVNE
NDC: 83257-009 | Form: INJECTION
Manufacturer: Biocon Biologics Inc.
Category: prescription | Type: HUMAN PRESCRIPTION DRUG LABEL
Date: 20250401

ACTIVE INGREDIENTS: BEVACIZUMAB 25 mg/1 mL
INACTIVE INGREDIENTS: TREHALOSE DIHYDRATE 60 mg/1 mL; POLYSORBATE 20 0.4 mg/1 mL; SODIUM PHOSPHATE, DIBASIC, ANHYDROUS 1.2 mg/1 mL; SODIUM PHOSPHATE, MONOBASIC, DIHYDRATE 5.8 mg/1 mL; WATER

HIGHLIGHTS OF PRESCRIBING INFORMATION

These highlights do not include all the information needed to use JOBEVNE safely and effectively. See full prescribing information for JOBEVNE.
JOBEVNE™(bevacizumab-nwgd) injection, for intravenous use
Initial U.S. Approval: 2025
JOBEVNE (bevacizumab-nwgd) is biosimilar* to AVASTIN® (bevacizumab)

1 INDICATIONS AND USAGE

Jobevne is a vascular endothelial growth factor inhibitor indicated for the treatment of:

- Metastatic colorectal cancer, in combination with intravenous fluorouracil-based chemotherapy for first-or second-line treatment. (1.1)
- Metastatic colorectal cancer, in combination with fluoropyrimidine-irinotecan-or fluoropyrimidine-oxaliplatin-based chemotherapy for second-line treatment in patients who have progressed on a first-line bevacizumab product-containing regimen. (1.1)

Limitations of Use: Jobevne is not indicated for adjuvant treatment of colon cancer. (1.1)

- Unresectable, locally advanced, recurrent or metastatic non-squamous non-small cell lung cancer, in combination with carboplatin and paclitaxel for first-line treatment. (1.2)
- Recurrent glioblastoma in adults. (1.3)
- Metastatic renal cell carcinoma in combination with interferon alfa. (1.4)
- Persistent, recurrent, or metastatic cervical cancer, in combination with paclitaxel and cisplatin, or paclitaxel and topotecan. (1.5)
- Epithelial ovarian, fallopian tube, or primary peritoneal cancer:
  - in combination with carboplatin and paclitaxel, followed by Jobevne as a single agent, for stage III or IV disease following initial surgical resection (1.6)
  - in combination with paclitaxel, pegylated liposomal doxorubicin, or topotecan for platinum-resistant recurrent disease who received no more than 2 prior chemotherapy regimens (1.6)
  - in combination with carboplatin and paclitaxel or carboplatin and gemcitabine, followed by Jobevne as a single agent, for platinum-sensitive recurrent disease (1.6)

2 DOSAGE AND ADMINISTRATION

Withhold for at least 28 days prior to elective surgery. Do not administer Jobevne for 28 days following major surgery and until adequate wound healing. (2.1)

Metastatic colorectal cancer (2.2)

- 5 mg/kg every 2 weeks with bolus-IFL
- 10 mg/kg every 2 weeks with FOLFOX4
- 5 mg/kg every 2 weeks or 7.5 mg/kg every 3 weeks with fluoropyrimidine-irinotecan- or fluoropyrimidine-oxaliplatin-based chemotherapy after progression on a first-line bevacizumab product-containing regimen

First-line non−squamous non−small cell lung cancer (2.3)

- 15 mg/kg every 3 weeks with carboplatin and paclitaxel

Recurrent glioblastoma (2.4)

- 10 mg/kg every 2 weeks

Metastatic renal cell carcinoma (2.5)

- 10 mg/kg every 2 weeks with interferon alfa

Persistent, recurrent, or metastatic cervical cancer (2.6)

- 15 mg/kg every 3 weeks with paclitaxel and cisplatin, or paclitaxel and topotecan

Stage III or IV epithelial ovarian, fallopian tube or primary peritoneal cancer following initial surgical resection (2.7)

- 15 mg/kg every 3 weeks with carboplatin and paclitaxel for up to 6 cycles, followed by 15 mg/kg every 3 weeks as a single agent, for a total of up to 22 cycles

Platinum-resistant recurrent epithelial ovarian, fallopian tube or primary peritoneal cancer (2.7)

- 10 mg/kg every 2 weeks with paclitaxel, pegylated liposomal doxorubicin, or topotecan given every week
- 15 mg/kg every 3 weeks with topotecan given every 3 weeks

Platinum-sensitive recurrent epithelial ovarian, fallopian tube, or primary peritoneal cancer (2.7)

- 15 mg/kg every 3 weeks with carboplatin and paclitaxel for 6-8 cycles, followed by 15 mg/kg every 3 weeks as a single agent
- 15 mg/kg every 3 weeks with carboplatin and gemcitabine for 6-10 cycles, followed by 15 mg/kg every 3 weeks as a single agent

Administer as an intravenous infusion after dilution. See full Prescribing Information for preparation and administration instructions and dosage modifications for adverse reactions (2.8, 2.9)

3 DOSAGE FORMS AND STRENGTHS

Injection: 100 mg/4 mL (25 mg/mL) or 400 mg/16 mL (25 mg/mL) in a single-dose vial (3)

4 CONTRAINDICATIONS

None (4)

5 WARNINGS AND PRECAUTIONS

- Gastrointestinal Perforations and Fistula: Discontinue for gastrointestinal perforations, tracheoesophageal fistula, Grade 4 fistula, or fistula formation involving any organ (5.1)
- Surgery and Wound Healing Complications: In patients who experience wound healing complications during Jobevne treatment, withhold Jobevne until adequate wound healing. Withhold for at least 28 days prior to elective surgery. Do not administer Jobevne for at least 28 days following a major surgery, and until adequate wound healing. The safety of resumption of bevacizumab products after resolution of wound healing complication has not been established. Discontinue for wound healing complications of necrotizing fasciitis (5.2)
- Hemorrhage: Severe or fatal hemorrhages have occurred. Do not administer for recent hemoptysis. Discontinue for Grade 3-4 hemorrhage (5.3)
- Arterial Thromboembolic Events (ATE): Discontinue for severe ATE. (5.4)
- Venous Thromboembolic Events (VTE): Discontinue for Grade 4 VTE. (5.5)
- Hypertension: Monitor blood pressure and treat hypertension. Withhold until medically controlled; resume once controlled. Discontinue for hypertensive crisis or hypertensive encephalopathy. (5.6)

- Posterior Reversible Encephalopathy Syndrome (PRES): Discontinue. (5.7)
- Renal Injury and Proteinuria: Monitor urine protein. Discontinue for nephrotic syndrome. Withhold until less than 2 grams of protein in urine. (5.8)
- Infusion-Related Reactions: Decrease rate for infusion-related reactions. Discontinue for severe infusion-related reactions and administer medical therapy. (5.9)
- Embryo-Fetal Toxicity: May cause fetal harm. Advise females of potential risk to fetus and need for use of effective contraception. (5.10, 8.1, 8.3)
- Ovarian Failure: Advise females of the potential risk. (5.11, 8.3)
- Congestive Heart Failure (CHF): Discontinue Jobevne in patients who develop CHF. (5.12)

6 ADVERSE REACTIONS

Most common adverse reactions incidence (incidence > 10%) are epistaxis, headache, hypertension, rhinitis, proteinuria, taste alteration, dry skin, hemorrhage, lacrimation disorder, back pain and exfoliative dermatitis. (6.1)

To report SUSPECTED ADVERSE REACTIONS, contact Biocon Biologics at 1-833-986-1468 or FDA at 1-800-FDA-1088 or www.fda.gov/medwatch.

8 USE IN SPECIFIC POPULATIONS

Lactation: Advise not to breastfeed. (8.2)

*Biosimilar means that the biological product is approved based on data demonstrating that it is highly similar to an FDA-approved biological product, known as a reference product, and that there are no clinically meaningful differences between the biosimilar product and the reference product. Biosimilarity of JOBEVNE has been demonstrated for the condition(s) of use (e.g., indication(s), dosing regimen(s), strength(s), dosage form(s), and route(s) of administration described in its Full Prescribing Information.

FULL PRESCRIBING INFORMATION

1 INDICATIONS AND USAGE

1.1 Metastatic Colorectal Cancer

Jobevne, in combination with intravenous fluorouracil-based chemotherapy, is indicated for the first-or second-line treatment of patients with metastatic colorectal cancer (mCRC).

Jobevne, in combination with fluoropyrimidine-irinotecan-or fluoropyrimidine-oxaliplatin-based chemotherapy, is indicated for the second-line treatment of patients with mCRC who have progressed on a first-line bevacizumab product-containing regimen.

Limitations of Use

Jobevne is not indicated for adjuvant treatment of colon cancer [see Clinical Studies (14.2)].

1.2 First-Line Non-Squamous Non–Small Cell Lung Cancer

Jobevne, in combination with carboplatin and paclitaxel, is indicated for the first-line treatment of patients with unresectable, locally advanced, recurrent or metastatic non–squamous non–small cell lung cancer (NSCLC).

1.3 Recurrent Glioblastoma

Jobevne is indicated for the treatment of recurrent glioblastoma (GBM) in adults.

1.4 Metastatic Renal Cell Carcinoma

Jobevne, in combination with interferon alfa, is indicated for the treatment of metastatic renal cell carcinoma (mRCC).

1.5 Persistent, Recurrent, or Metastatic Cervical Cancer

Jobevne, in combination with paclitaxel and cisplatin or paclitaxel and topotecan, is indicated for the treatment of patients with persistent, recurrent, or metastatic cervical cancer.

1.6 Epithelial Ovarian, Fallopian Tube, or Primary Peritoneal Cancer

Jobevne, in combination with carboplatin and paclitaxel, followed by Jobevne as a single agent, is indicated for the treatment of patients with stage III or IV epithelial ovarian, fallopian tube, or primary peritoneal cancer following initial surgical resection.

Jobevne, in combination with paclitaxel, pegylated liposomal doxorubicin, or topotecan, is indicated for the treatment of patients with platinum-resistant recurrent epithelial ovarian, fallopian tube or primary peritoneal cancer who received no more than 2 prior chemotherapy regimens.

Jobevne, in combination with carboplatin and paclitaxel, or with carboplatin and gemcitabine, followed by Jobevne as a single agent, is indicated for the treatment of patients with platinum-sensitive recurrent epithelial ovarian, fallopian tube, or primary peritoneal cancer.

2 DOSAGE AND ADMINISTRATION

2.1 Important Administration Information

Withhold for at least 28 days prior to elective surgery. Do not administer Jobevne until at least 28 days following major surgery and until adequate wound healing.

2.2 Metastatic Colorectal Cancer

The recommended dosage when Jobevne is administered in combination with intravenous fluorouracil-based chemotherapy is:

- 5 mg/kg intravenously every 2 weeks in combination with bolus-IFL.
- 10 mg/kg intravenously every 2 weeks in combination with FOLFOX4.
- 5 mg/kg intravenously every 2 weeks or 7.5 mg/kg intravenously every 3 weeks in combination with fluoropyrimidine-irinotecan-or fluoropyrimidine-oxaliplatin-based chemotherapy in patients who have progressed on a first-line bevacizumab product-containing regimen.

2.3 First-Line Non-Squamous Non-Small Cell Lung Cancer

The recommended dosage is 15 mg/kg intravenously every 3 weeks in combination with carboplatin and paclitaxel.

2.4 Recurrent Glioblastoma

The recommended dosage is 10 mg/kg intravenously every 2 weeks.

2.5 Metastatic Renal Cell Carcinoma

The recommended dosage is 10 mg/kg intravenously every 2 weeks in combination with interferon alfa.

2.6 Persistent, Recurrent, or Metastatic Cervical Cancer

The recommended dosage is 15 mg/kg intravenously every 3 weeks in combination with paclitaxel and cisplatin or in combination with paclitaxel and topotecan.

2.7 Epithelial Ovarian, Fallopian Tube or Primary Peritoneal Cancer

Stage III or IV Disease Following Initial Surgical Resection

The recommended dosage is 15 mg/kg intravenously every 3 weeks in combination with carboplatin and paclitaxel for up to 6 cycles, followed by Jobevne 15 mg/kg every 3 weeks as a single agent for a total of up to 22 cycles or until disease progression, whichever occurs earlier.

Recurrent Disease

Platinum Resistant

The recommended dosage is 10 mg/kg intravenously every 2 weeks in combination with paclitaxel, pegylated liposomal doxorubicin, or topotecan (every week).

The recommended dosage is 15 mg/kg intravenously every 3 weeks in combination with topotecan (every 3 weeks).

Platinum Sensitive

The recommended dosage is 15 mg/kg intravenously every 3 weeks, in combination with carboplatin and paclitaxel for 6 to 8 cycles, followed by Jobevne 15 mg/kg every 3 weeks as a single agent until disease progression.

The recommended dosage is 15 mg/kg intravenously every 3 weeks, in combination with carboplatin and gemcitabine for 6 to 10 cycles, followed by Jobevne 15 mg/kg every 3 weeks as a single agent until disease progression.

2.8 Dosage Modifications for Adverse Reactions

Table 1 describes dosage modifications for specific adverse reactions . No dose reductions for Jobevne are recommended.

Table 1: Dosage Modifications for Adverse Reactions
Adverse Reaction | Severity | Dosage Modification
Gastrointestinal Perforations and Fistulae [see Warnings and Precautions (5.1)]. | - Gastrointestinal perforation, any grade - Tracheoesophageal fistula, any grade - Fistula, Grade 4 - Fistula formation involving any internal organ | Discontinue Jobevne
Wound Healing Complications [see Warnings and Precautions (5.2)]. | - Any | Withhold Jobevne until adequate wound healing. The safety of resumption of bevacizumab products after resolution of wound healing complications has not been established
Wound Healing Complications [see Warnings and Precautions (5.2)]. | - Necrotizing fasciitis | Discontinue Jobevne
Hemorrhage [see Warnings and Precautions (5.3)]. | - Grade 3 or 4 | Discontinue Jobevne
Hemorrhage [see Warnings and Precautions (5.3)]. | - Recent history of hemoptysis of 1/2 teaspoon (2.5 mL) or more | Withhold Jobevne
Thromboembolic Events [see Warnings and Precautions (5.4, 5.5)]. | - Arterial thromboembolism, severe | Discontinue Jobevne
Thromboembolic Events [see Warnings and Precautions (5.4, 5.5)]. | - Venous thromboembolism, Grade 4 | Discontinue Jobevne
Hypertension [see Warnings and Precautions (5.6)]. | - Hypertensive crisis - Hypertensive encephalopathy | Discontinue Jobevne
Hypertension [see Warnings and Precautions (5.6)]. | - Hypertension, severe (such as Grade 3 and above) | Withhold Jobevne until controlled with medical management; resume once controlled
Posterior Reversible Encephalopathy Syndrome (PRES) [see Warnings and Precautions (5.7)]. | - Any | Discontinue Jobevne
Renal Injury and Proteinuria [see Warnings and Precautions (5.8)]. | - Nephrotic syndrome | Discontinue Jobevne
Renal Injury and Proteinuria [see Warnings and Precautions (5.8)]. | - Proteinuria greater than or equal to 2 grams per 24 hours in absence of nephrotic syndrome | Withhold Jobevne until proteinuria less than 2 grams per 24 hours
Infusion-Related Reactions [see Warnings and Precautions (5.9)]. | - Severe | Discontinue Jobevne
Infusion-Related Reactions [see Warnings and Precautions (5.9)]. | - Clinically significant | Interrupt infusion; resume at a decreased rate of infusion after symptoms resolve
Infusion-Related Reactions [see Warnings and Precautions (5.9)]. | - Mild, clinically insignificant | Decrease infusion rate
Congestive Heart Failure [see Warnings and Precautions (5.12)]. | Any | Discontinue Jobevne

2.9 Preparation and Administration

Preparation

- Use appropriate aseptic technique.
- Use sterile needle and syringe to prepare Jobevne.
- Parenteral drug products should be inspected visually for particulate matter and discoloration prior to administration, whenever solution and container permit. Discard vial if solution is cloudy, discolored or contains particulate matter.
- Withdraw necessary amount of Jobevne and dilute in a total volume of 100 mL of 0.9% Sodium Chloride Injection, USP. DO NOT ADMINISTER OR MIX WITH DEXTROSE SOLUTION.
- Discard any unused portion left in a vial, as the product contains no preservatives.
- Diluted Jobevne solution may be stored at 2°C to 8°C (36°F to 46°F) for up to 8 hours, if not used immediately.
- No incompatibilities between Jobevne and polyvinylchloride or polyolefin bags have been observed.

Administration

- Administer as an intravenous infusion.
- First infusion: Administer infusion over 90 minutes.
- Subsequent infusions: Administer second infusion over 60 minutes if first infusion is tolerated. Administer all subsequent infusions over 30 minutes if second infusion over 60 minutes is tolerated.

3 DOSAGE FORMS AND STRENGTHS

Injection: 100 mg/4 mL (25 mg/mL) or 400 mg/16 mL (25 mg/mL) clear to slightly opalescent, colorless to pale brown solution in a single-dose vial.

4 CONTRAINDICATIONS

None.

5 WARNINGS AND PRECAUTIONS

5.1 Gastrointestinal Perforations and Fistulae

Serious, and sometimes fatal, gastrointestinal perforation occurred at a higher incidence in patients receiving bevacizumab products compared to patients receiving chemotherapy. The incidence ranged from 0.3% to 3% across clinical studies, with the highest incidence in patients with a history of prior pelvic radiation. Perforation can be complicated by intra-abdominal abscess, fistula formation, and the need for diverting ostomies. The majority of perforations occurred within 50 days of the first dose [see Adverse Reactions (6.1)].

Serious fistulae (including, tracheoesophageal, bronchopleural, biliary, vaginal, renal and bladder sites) occurred at a higher incidence in patients receiving bevacizumab products compared to patients receiving chemotherapy. The incidence ranged from < 1% to 1.8% across clinical studies, with the highest incidence in patients with cervical cancer. The majority of fistulae occurred within 6 months of the first dose. Patients who develop a gastrointestinal vaginal fistula may also have a bowel obstruction and require surgical intervention, as well as a diverting ostomy.

Avoid Jobevne in patients with ovarian cancer who have evidence of recto-sigmoid involvement by pelvic examination or bowel involvement on CT scan or clinical symptoms of bowel obstruction. Discontinue in patients who develop gastrointestinal perforation, tracheoesophageal fistula or any Grade 4 fistula. Discontinue in patients with fistula formation involving any internal organ.

5.2 Surgery and Wound Healing Complications

In a controlled clinical study in which bevacizumab was not administered within 28 days of major surgical procedures, the incidence of wound healing complications, including serious and fatal complications, was 15% in patients with mCRC who underwent surgery while receiving bevacizumab and 4% in patients who did not receive bevacizumab. In a controlled clinical study in patients with relapsed or recurrent GBM, the incidence of wound healing events was 5% in patients who received bevacizumab and 0.7% in patients who did not receive bevacizumab [see Adverse Reactions (6.1)].

In patients who experience wound healing complications during Jobevne treatment, withhold Jobevne until adequate wound healing. Withhold for at least 28 days prior to elective surgery. Do not administer for at least 28 days following major surgery and until adequate wound healing. The safety of resumption of bevacizumab products after resolution of wound healing complications has not been established [see Dosage and Administration (2.8)].

Necrotizing fasciitis including fatal cases, has been reported in patients receiving bevacizumab, usually secondary to wound healing complications, gastrointestinal perforation or fistula formation. Discontinue Jobevne in patients who develop necrotizing fasciitis.

5.3 Hemorrhage

Bevacizumab products can result in two distinct patterns of bleeding: minor hemorrhage, which is most commonly Grade 1 epistaxis, and serious hemorrhage, which in some cases has been fatal. Severe or fatal hemorrhage, including hemoptysis, gastrointestinal bleeding, hematemesis, CNS hemorrhage, epistaxis, and vaginal bleeding, occurred up to 5-fold more frequently in patients receiving bevacizumab compared to patients receiving chemotherapy alone. Across clinical studies, the incidence of Grades 3-5 hemorrhagic events ranged from 0.4% to 7% in patients receiving bevacizumab [see Adverse Reactions (6.1)].

Serious or fatal pulmonary hemorrhage occurred in 31% of patients with squamous NSCLC and 4% of patients with non-squamous NSCLC receiving bevacizumab with chemotherapy compared to none of the patients receiving chemotherapy alone.

Do not administer Jobevne to patients with recent history of hemoptysis of 1/2 teaspoon or more of red blood. Discontinue in patients who develop a Grades 3-4 hemorrhage.

5.4 Arterial Thromboembolic Events

Serious, sometimes fatal, arterial thromboembolic events (ATE) including cerebral infarction, transient ischemic attacks, myocardial infarction, and angina, occurred at a higher incidence in patients receiving bevacizumab compared to patients receiving chemotherapy. Across clinical studies, the incidence of Grades 3-5 ATE was 5% in patients receiving bevacizumab with chemotherapy compared to ≤ 2% in patients receiving chemotherapy alone; the highest incidence occurred in patients with GBM. The risk of developing ATE was increased in patients with a history of arterial thromboembolism, diabetes, or > 65 years [see Use in Specific Populations (8.5)].

Discontinue in patients who develop a severe ATE. The safety of reinitiating bevacizumab products after an ATE is resolved is not known.

5.5 Venous Thromboembolic Events

An increased risk of venous thromboembolic events (VTE) was observed across clinical studies [see Adverse Reactions (6.1)]. In Study GOG-0240, Grades 3-4 VTE occurred in 11% of patients receiving bevacizumab with chemotherapy compared with 5% of patients receiving chemotherapy alone. In EORTC 26101, the incidence of Grades 3-4 VTE was 5% in patients receiving bevacizumab with chemotherapy compared to 2% in patients receiving chemotherapy alone.

Discontinue Jobevne in patients with a Grade 4 VTE, including pulmonary embolism.

5.6 Hypertension

Severe hypertension occurred at a higher incidence in patients receiving bevacizumab products as compared to patients receiving chemotherapy alone. Across clinical studies, the incidence of Grades 3-4 hypertension ranged from 5% to 18%.

Monitor blood pressure every two to three weeks during treatment with Jobevne. Treat with appropriate anti-hypertensive therapy and monitor blood pressure regularly. Continue to monitor blood pressure at regular intervals in patients with Jobevne-induced or -exacerbated hypertension after discontinuing Jobevne. Withhold Jobevne in patients with severe hypertension (such as Grade 3 and above) until controlled with medical management; resume once controlled with medical management. Discontinue in patients who develop hypertensive crisis or hypertensive encephalopathy.

5.7 Posterior Reversible Encephalopathy Syndrome

Posterior reversible encephalopathy syndrome (PRES) was reported in < 0.5% of patients across clinical studies. The onset of symptoms occurred from 16 hours to 1 year after the first dose. PRES is a neurological disorder which can present with headache, seizure, lethargy, confusion, blindness and other visual and neurologic disturbances. Mild to severe hypertension may be present. Magnetic resonance imaging is necessary to confirm the diagnosis of PRES.

Discontinue Jobevne in patients who develop PRES. Symptoms usually resolve or improve within days after discontinuing bevacizumab products, although some patients have experienced ongoing neurologic sequelae. The safety of reinitiating bevacizumab products in patients who developed PRES is not known.

5.8 Renal Injury and Proteinuria

The incidence and severity of proteinuria was higher in patients receiving bevacizumab as compared to patients receiving chemotherapy. Grade 3 (defined as urine dipstick 4+ or > 3.5 grams of protein per 24 hours) to Grade 4 (defined as nephrotic syndrome) ranged from 0.7% to 7% in clinical studies. The overall incidence of proteinuria (all grades) was only adequately assessed in Study BO17705, in which the incidence was 20%. Median onset of proteinuria was 5.6 months (15 days to 37 months) after initiating bevacizumab. Median time to resolution was 6.1 months (95% CI: 2.8, 11.3). Proteinuria did not resolve in 40% of patients after median follow-up of 11.2 months and required discontinuation of bevacizumab in 30% of the patients who developed proteinuria [see Adverse Reactions (6.1)].

In an exploratory, pooled analysis of patients from seven randomized clinical studies, 5% of patients receiving bevacizumab with chemotherapy experienced Grades 2-4 (defined as urine dipstick 2+ or greater or > 1 gram of protein per 24 hours or nephrotic syndrome) proteinuria. Grades 2-4 proteinuria resolved in 74% of patients. Bevacizumab was reinitiated in 42% of patients. Of the 113 patients who reinitiated bevacizumab, 48% experienced a second episode of Grades 2-4 proteinuria.

Nephrotic syndrome occurred in < 1% of patients receiving bevacizumab across clinical studies, in some instances with fatal outcome. In a published case series, kidney biopsy of 6 patients with proteinuria showed findings consistent with thrombotic microangiopathy. Results of a retrospective analysis of 5805 patients who received bevacizumab with chemotherapy and 3713 patients who received chemotherapy alone, showed higher rates of elevated serum creatinine levels (between 1.5 to 1.9 times baseline levels) in patients who received bevacizumab. Serum creatinine levels did not return to baseline in approximately one-third of patients who received bevacizumab.

Monitor proteinuria by dipstick urine analysis for the development or worsening of proteinuria with serial urinalyses during Jobevne therapy. Patients with a 2+ or greater urine dipstick reading should undergo further assessment with a 24-hour urine collection. Withhold for proteinuria greater than or equal to 2 grams per 24 hours and resume when less than 2 grams per 24 hours. Discontinue in patients who develop nephrotic syndrome.

Data from a postmarketing safety study showed poor correlation between UPCR (Urine Protein/Creatinine Ratio) and 24-hour urine protein [Pearson Correlation 0.39 (95% CI: 0.17, 0.57)].

5.9 Infusion-Related Reactions

Infusion-related reactions reported across clinical studies and postmarketing experience include hypertension, hypertensive crises associated with neurologic signs and symptoms, wheezing, oxygen desaturation, Grade 3 hypersensitivity, anaphylactoid/anaphylactic reactions, chest pain, headaches, rigors, and diaphoresis. In clinical studies, infusion-related reactions with the first dose occurred in < 3% of patients and severe reactions occurred in 0.4% of patients.

Decrease the rate of infusion for mild, clinically insignificant infusion-related reactions. Interrupt the infusion in patients with clinically significant infusion-related reactions and consider resuming at a slower rate following resolution. Discontinue in patients who develop a severe infusion-related reaction and administer appropriate medical therapy (e.g., epinephrine, corticosteroids, intravenous antihistamines, bronchodilators and/or oxygen).

5.10 Embryo-Fetal Toxicity

Based on its mechanism of action and findings from animal studies, bevacizumab products may cause fetal harm when administered to pregnant women. Congenital malformations were observed with the administration of bevacizumab to pregnant rabbits during organogenesis every 3 days at a dose as low as a clinical dose of 10 mg/kg. Furthermore, animal models link angiogenesis and VEGF and VEGFR2 to critical aspects of female reproduction, embryo-fetal development, and postnatal development. Advise pregnant women of the potential risk to a fetus. Advise females of reproductive potential to use effective contraception during treatment with Jobevne and for 6 months after the last dose [see Use in Specific Populations (8.1, 8.3)].

5.11 Ovarian Failure

The incidence of ovarian failure was 34% vs. 2% in premenopausal women receiving bevacizumab with chemotherapy as compared to those receiving chemotherapy alone for adjuvant treatment of a solid tumor. After discontinuing bevacizumab, recovery of ovarian function at all time points during the post-treatment period was demonstrated in 22% of women receiving bevacizumab. Recovery of ovarian function is defined as resumption of menses, a positive serum β-HCG pregnancy test, or an FSH level < 30 mIU/mL during the post-treatment period. Long-term effects of bevacizumab products on fertility are unknown. Inform females of reproductive potential of the risk of ovarian failure prior to initiating Jobevne [see Adverse Reactions (6.1), Use in Specific Populations (8.3)].

5.12 Congestive Heart Failure (CHF)

Jobevne is not indicated for use with anthracycline-based chemotherapy. The incidence of Grade ≥ 3 left ventricular dysfunction was 1% in patients receiving bevacizumab compared to 0.6% of patients receiving chemotherapy alone. Among patients who received prior anthracycline treatment, the rate of CHF was 4% for patients receiving bevacizumab with chemotherapy as compared to 0.6% for patients receiving chemotherapy alone.

In previously untreated patients with a hematological malignancy, the incidence of CHF and decline in left ventricular ejection fraction (LVEF) were increased in patients receiving bevacizumab with anthracycline-based chemotherapy compared to patients receiving placebo with the same chemotherapy regimen. The proportion of patients with a decline in LVEF from baseline of ≥ 20% or a decline from baseline of 10% to < 50%, was 10% in patients receiving bevacizumab with chemotherapy compared to 5% in patients receiving chemotherapy alone. Time to onset of left-ventricular dysfunction or CHF was 1 to 6 months after the first dose in at least 85% of the patients and was resolved in 62% of the patients who developed CHF in the bevacizumab arm compared to 82% in the placebo arm. Discontinue Jobevne in patients who develop CHF.

6 ADVERSE REACTIONS

The following clinically significant adverse reactions are described elsewhere in the labeling:

- Gastrointestinal Perforations and Fistulae [see Warnings and Precautions (5.1)].
- Surgery and Wound Healing Complications [see Warnings and Precautions (5.2)].
- Hemorrhage [see Warnings and Precautions (5.3)].
- Arterial Thromboembolic Events [see Warnings and Precautions (5.4)].
- Venous Thromboembolic Events [see Warnings and Precautions (5.5)].
- Hypertension [see Warnings and Precautions (5.6)].
- Posterior Reversible Encephalopathy Syndrome [see Warnings and Precautions (5.7)].
- Renal Injury and Proteinuria [see Warnings and Precautions (5.8)].
- Infusion-Related Reactions [see Warnings and Precautions (5.9)].
- Ovarian Failure [see Warnings and Precautions (5.11)].
- Congestive Heart Failure [see Warnings and Precautions (5.12)].

6.1 Clinical Trials Experience

Because clinical studies are conducted under widely varying conditions, adverse reaction rates observed in the clinical studies of a drug cannot be directly compared to rates in the clinical studies of another drug and may not reflect the rates observed in practice.

The safety data in Warnings and Precautions and described below reflect exposure to bevacizumab in 4463 patients including those with mCRC (AVF2107g, E3200), non-squamous NSCLC (E4599), GBM (EORTC 26101), mRCC (BO17705), cervical cancer (GOG-0240), and epithelial ovarian, fallopian tube, or primary peritoneal cancer (MO22224 AVF4095, GOG-0213, and GOG-0218) or another cancers at the recommended dose and schedule for a median of 6 to 23 doses. The most common adverse reactions observed in patients receiving bevacizumab as a single agent or in combination with other anti-cancer therapies at a rate > 10% were epistaxis, headache, hypertension, rhinitis, proteinuria, taste alteration, dry skin, hemorrhage, lacrimation disorder, back pain, and exfoliative dermatitis.

Across clinical studies, bevacizumab was discontinued in 8% to 22% of patients because of adverse reactions [see Clinical Studies (14)].

Metastatic Colorectal Cancer

In Combination with bolus-IFL

The safety of bevacizumab was evaluated in 392 patients who received at least one dose of bevacizumab in a double-blind, active-controlled study (AVF2107g), which compared bevacizumab (5 mg/kg every 2 weeks) with bolus-IFL to placebo with bolus-IFL in patients with mCRC [see Clinical Studies (14.1)]. Patients were randomized (1:1:1) to placebo with bolus-IFL, bevacizumab with bolus-IFL, or bevacizumab with fluorouracil and leucovorin. The demographics of the safety population were similar to the demographics of the efficacy population. All Grades 3−4 adverse reactions and selected Grades 1−2 adverse reactions (i.e., hypertension, proteinuria, thromboembolic events) were collected in the entire study population. Adverse reactions are presented in Table 2.

Table 2: Grades 3-4 Adverse Reactions Occurring at Higher Incidence (≥ 2%) in Patients Receiving Bevacizumab vs. Placebo in Study AVF2107g
Adverse Reaction [NCI-CTC version 3.] | Bevacizumab with IFL; (N = 392) | Placebo with IFL; (N = 396)
Hematology
Leukopenia | 37% | 31%
Neutropenia | 21% | 14%
Gastrointestinal
Diarrhea | 34% | 25%
Abdominal pain | 8% | 5%
Constipation | 4% | 2%
Vascular
Hypertension | 12% | 2%
Deep vein thrombosis | 9% | 5%
Intra-abdominal thrombosis | 3% | 1%
Syncope | 3% | 1%
General
Asthenia | 10% | 7%
Pain | 8% | 5%

In Combination with FOLFOX4

The safety of bevacizumab was evaluated in 521 patients in an open-label, active-controlled study (E3200) in patients who were previously treated with irinotecan and fluorouracil for initial therapy for mCRC. Patients were randomized (1:1:1) to FOLFOX4, bevacizumab (10 mg/kg every 2 weeks prior to FOLFOX4 on Day 1) with FOLFOX4, or bevacizumab alone (10 mg/kg every 2 weeks). Bevacizumab was continued until disease progression or unacceptable toxicity.

The demographics of the safety population were similar to the demographics of the efficacy population.

Selected Grades 3−5 non-hematologic and Grades 4−5 hematologic occurring at a higher incidence (≥ 2%) in patients receiving bevacizumab with FOLFOX4 compared to FOLFOX4 alone were fatigue (19% vs. 13%), diarrhea (18% vs. 13%), sensory neuropathy (17% vs. 9%), nausea (12% vs. 5%), vomiting (11% vs. 4%), dehydration (10% vs. 5%), hypertension (9% vs. 2%), abdominal pain (8% vs. 5%), hemorrhage (5% vs. 1%), other neurological (5% vs. 3%), ileus (4% vs. 1%) and headache (3% vs. 0%). These data are likely to under-estimate the true adverse reaction rates due to the reporting mechanisms.

First-Line Non-Squamous Non-Small Cell Lung Cancer

The safety of bevacizumab was evaluated as first-line treatment in 422 patients with unresectable NSCLC who received at least one dose of bevacizumab in an active-controlled, open-label, multicenter trial (E4599) [see Clinical Studies (14.3)]. Chemotherapy naïve patients with locally advanced, metastatic or recurrent non–squamous NSCLC were randomized (1:1) to receive six 21-day cycles of paclitaxel and carboplatin with or without bevacizumab (15 mg/kg every 3 weeks). After completion or upon discontinuation of chemotherapy, patients randomized to receive bevacizumab continued to receive bevacizumab alone until disease progression or until unacceptable toxicity. The trial excluded patients with predominant squamous histology (mixed cell type tumors only), CNS metastasis, gross hemoptysis (1/2 teaspoon or more of red blood), unstable angina, or receiving therapeutic anticoagulation. The demographics of the safety population were similar to the demographics of the efficacy population.

Only Grades 3-5 non-hematologic and Grades 4-5 hematologic adverse reactions were collected. Grades 3-5 non-hematologic and Grades 4-5 hematologic adverse reactions occurring at a higher incidence (≥ 2%) in patients receiving bevacizumab with paclitaxel and carboplatin compared with patients receiving chemotherapy alone were neutropenia (27% vs. 17%), fatigue (16% vs. 13%), hypertension (8% vs. 0.7%), infection without neutropenia (7% vs. 3%), venous thromboembolism (5% vs. 3%), febrile neutropenia (5% vs. 2%), pneumonitis/pulmonary infiltrates (5% vs. 3%), infection with Grade 3 or 4 neutropenia (4% vs. 2%), hyponatremia (4% vs. 1%), headache (3% vs. 1%) and proteinuria (3% vs. 0%).

Recurrent Glioblastoma

The safety of bevacizumab was evaluated in a multicenter, randomized, open-label study (EORTC 26101) in patients with recurrent GBM following radiotherapy and temozolomide of whom 278 patients received at least one dose of bevacizumab and are considered safety evaluable [see Clinical Studies (14.4)]. Patients were randomized (2:1) to receive bevacizumab (10 mg/kg every 2 weeks) with lomustine or lomustine alone until disease progression or unacceptable toxicity. The demographics of the safety population were similar to the demographics of the efficacy population. In the bevacizumab with lomustine arm, 22% of patients discontinued treatment due to adverse reactions compared with 10% of patients in the lomustine arm. In patients receiving bevacizumab with lomustine, the adverse reaction profile was similar to that observed in other approved indications.

Metastatic Renal Cell Carcinoma

The safety of bevacizumab was evaluated in 337 patients who received at least one dose of bevacizumab in a multicenter, double-blind study (BO17705) in patients with mRCC. Patients who had undergone a nephrectomy were randomized (1:1) to receive either bevacizumab (10 mg/kg every 2 weeks) or placebo with interferon alfa [see Clinical Studies (14.5)]. Patients were treated until disease progression or unacceptable toxicity. The demographics of the safety population were similar to the demographics of the efficacy population.

Grades 3-5 adverse reactions occurring at a higher incidence (> 2%) were fatigue (13% vs. 8%), asthenia (10% vs. 7%), proteinuria (7% vs. 0%), hypertension (6% vs. 1%; including hypertension and hypertensive crisis), and hemorrhage (3% vs. 0.3%; including epistaxis, small intestinal hemorrhage, aneurysm ruptured, gastric ulcer hemorrhage, gingival bleeding, hemoptysis, hemorrhage intracranial, large intestinal hemorrhage, respiratory tract hemorrhage, and traumatic hematoma). Adverse reactions are presented in Table 3.

Table 3: Grades 1-5 Adverse Reactions Occurring at Higher Incidence (≥ 5%) of Patients Receiving Bevacizumab vs. Placebo with Interferon Alfa in Study BO17705
Adverse Reaction [NCI-CTC version 3.] | Bevacizumab with Interferon Alfa; (N = 337) | Placebo with Interferon Alfa; (N = 304)
Metabolism and nutrition
Decreased appetite | 36% | 31%
Weight loss | 20% | 15%
General
Fatigue | 33% | 27%
Vascular
Hypertension | 28% | 9%
Respiratory, thoracic and mediastinal
Epistaxis | 27% | 4%
Dysphonia | 5% | 0%
Nervous system
Headache | 24% | 16%
Gastrointestinal
Diarrhea | 21% | 16%
Renal and urinary
Proteinuria | 20% | 3%
Musculoskeletal and connective tissue
Myalgia | 19% | 14%
Back pain | 12% | 6%

The following adverse reactions were reported at a 5-fold greater incidence in patients receiving bevacizumab with interferon-alfa compared to patients receiving placebo with interferon-alfa and not represented in Table 3: gingival bleeding (13 patients vs. 1 patient); rhinitis (9 vs. 0); blurred vision (8 vs. 0); gingivitis (8 vs. 1); gastroesophageal reflux disease (8 vs. 1); tinnitus (7 vs. 1); tooth abscess (7 vs. 0); mouth ulceration (6 vs. 0); acne (5 vs. 0); deafness (5 vs. 0); gastritis (5 vs. 0); gingival pain (5 vs. 0) and pulmonary embolism (5 vs. 1).

Persistent, Recurrent, or Metastatic Cervical Cancer

The safety of bevacizumab was evaluated in 218 patients who received at least one dose of bevacizumab in a multicenter study (GOG-0240) in patients with persistent, recurrent, or metastatic cervical cancer [see Clinical Studies (14.6)]. Patients were randomized (1:1:1:1) to receive paclitaxel and cisplatin with or without bevacizumab (15 mg/kg every 3 weeks), or paclitaxel and topotecan with or without bevacizumab (15 mg/kg every 3 weeks). The demographics of the safety population were similar to the demographics of the efficacy population.

Grades 3-4 adverse reactions occurring at a higher incidence (≥ 2%) in 218 patients receiving bevacizumab with chemotherapy compared to 222 patients receiving chemotherapy alone were abdominal pain (12% vs. 10%), hypertension (11% vs. 0.5%), thrombosis (8% vs. 3%), diarrhea (6% vs. 3%), anal fistula (4% vs. 0%), proctalgia (3% vs. 0%), urinary tract infection (8% vs. 6%), cellulitis (3% vs. 0.5%), fatigue (14% vs. 10%), hypokalemia (7% vs. 4%), hyponatremia (4% vs. 1%), dehydration (4% vs. 0.5%), neutropenia (8% vs. 4%), lymphopenia (6% vs. 3%), back pain (6% vs. 3%), and pelvic pain (6% vs. 1%). Adverse reactions are presented in Table 4.

Table 4: Grades 1-4 Adverse Reactions Occurring at Higher Incidence (≥ 5%) in Patients Receiving Bevacizumab with Chemotherapy vs. Chemotherapy Alone in Study GOG-0240
Adverse Reaction [NCI-CTC version 3.] | Bevacizumab with Chemotherapy; (N = 218) | Chemotherapy; (N = 222)
General
Fatigue | 80% | 75%
Peripheral edema | 15% | 22%
Metabolism and nutrition
Decreased appetite | 34% | 26%
Hyperglycemia | 26% | 19%
Hypomagnesemia | 24% | 15%
Weight loss | 21% | 7%
Hyponatremia | 19% | 10%
Hypoalbuminemia | 16% | 11%
Vascular
Hypertension | 29% | 6%
Thrombosis | 10% | 3%
Infections
Urinary tract infection | 22% | 14%
Infection | 10% | 5%
Nervous system
Headache | 22% | 13%
Dysarthria | 8% | 1%
Psychiatric
Anxiety | 17% | 10%
Respiratory, thoracic and mediastinal
Epistaxis | 17% | 1%
Renal and urinary
Increased blood creatinine | 16% | 10%
Proteinuria | 10% | 3%
Gastrointestinal
Stomatitis | 15% | 10%
Proctalgia | 6% | 1%
Anal fistula | 6% | 0%
Reproductive system and breast
Pelvic pain | 14% | 8%
Hematology
Neutropenia | 12% | 6%
Lymphopenia | 12% | 5%

Epithelial Ovarian, Fallopian Tube or Primary Peritoneal Cancer

Stage III or IV Following Initial Surgical Resection

The safety of bevacizumab was evaluated in GOG-0218, a multicenter, randomized, double-blind, placebo controlled, three arm study, which evaluated the addition of bevacizumab to carboplatin and paclitaxel for the treatment of patients with stage III or IV epithelial ovarian, fallopian tube or primary peritoneal cancer following initial surgical resection [see Clinical Studies (14.7)]. Patients were randomized (1:1:1) to carboplatin and paclitaxel without bevacizumab (CPP), carboplatin and paclitaxel with bevacizumab for up to six cycles (CPB15), or carboplatin and paclitaxel with bevacizumab for six cycles followed by bevacizumab as a single agent for up to 16 additional doses (CPB15+). Bevacizumab was given at 15 mg/kg every three weeks. On this trial, 1215 patients received at least one dose of bevacizumab. The demographics of the safety population were similar to the demographics of the efficacy population.

Grades 3-4 adverse reactions occurring at a higher incidence (≥2%) in either of the bevacizumab arms versus thecontrol arm were fatigue (CPB15+ -9%, CPB15 -6%, CPP -6%), hypertension (CPB15+ -10%, CPB15 -6%,CPP -2%), thrombocytopenia (CPB15+ -21%, CPB15 -20%, CPP -15%) and leukopenia (CPB15+ -51%,CPB15 -53%, CPP -50%). Adverse reactions are presented in Table 5.

Table 5: Grades 1-5 Adverse Reactions Occurring at Higher Incidence (≥ 5%) in Patients Receiving Bevacizumab with Chemotherapy vs. Chemotherapy Alone in GOG-0218
Adverse Reaction [NCI-CTC version 3,] | Bevacizumab with carboplatin and paclitaxel followed by bevacizumab alone [CPB15^+,]; N = (608) | Bevacizumab with carboplatin and paclitaxel [CPB15,]; (N = 607) | Carboplatin and paclitaxel [CPP]; (N = 602)
General
Fatigue | 80% | 72% | 73%
Gastrointestinal
Nausea | 58% | 53% | 51%
Diarrhea | 38% | 40% | 34%
Stomatitis | 25% | 19% | 14%
Musculoskeletal and connective tissue
Arthralgia | 41% | 33% | 35%
Pain in extremity | 25% | 19% | 17%
Muscular weakness | 15% | 13% | 9%
Nervous system
Headache | 34% | 26% | 21%
Dysarthria | 12% | 10% | 2%
Vascular
Hypertension | 32% | 24% | 14%
Respiratory, thoracic and mediastinal
Epistaxis | 31% | 30% | 9%
Dyspnea | 26% | 28% | 20%
Nasal mucosal disorder | 10% | 7% | 4%

Platinum-Resistant Recurrent Epithelial Ovarian, Fallopian Tube, or Primary Peritoneal Cancer

The safety of bevacizumab was evaluated in 179 patients who received at least one dose of bevacizumab in a multicenter, open-label study (MO22224) in which patients were randomized (1:1) to bevacizumab with chemotherapy or chemotherapy alone in patients with platinum resistant, recurrent epithelial ovarian, fallopian tube, or primary peritoneal cancer that recurred within < 6 months from the most recent platinum based therapy [see Clinical Studies (14.8)]. Patients were randomized to receive bevacizumab 10 mg/kg every 2 weeks or 15 mg/kg every 3 weeks. Patients had received no more than 2 prior chemotherapy regimens. The trial excluded patients with evidence of recto-sigmoid involvement by pelvic examination or bowel involvement on CT scan or clinical symptoms of bowel obstruction. Patients were treated until disease progression or unacceptable toxicity. Forty percent of patients on the chemotherapy alone arm received bevacizumab alone upon progression. The demographics of the safety population were similar to the demographics of the efficacy population.

Grades 3-4 adverse reactions occurring at a higher incidence (≥ 2%) in 179 patients receiving bevacizumab with chemotherapy compared to 181 patients receiving chemotherapy alone were hypertension (6.7% vs. 1.1%) and palmar-plantar erythrodysaesthesia syndrome (4.5% vs. 1.7%).

Adverse reactions are presented in Table 6.

Table 6: Grades 2-4 Adverse Reactions Occurring at Higher Incidence (≥ 5%) in Patients Receiving Bevacizumab with Chemotherapy vs. Chemotherapy Alone in Study MO22224
Adverse Reaction [NCI-CTC version 3.] | Bevacizumab with Chemotherapy; (N = 179) | Chemotherapy; (N = 181)
Hematology
Neutropenia | 31% | 25%
Vascular
Hypertension | 19% | 6%
Nervous system
Peripheral sensory neuropathy | 18% | 7%
General
Mucosal inflammation | 13% | 6%
Renal and urinary
Proteinuria | 12% | 0.6%
Skin and subcutaneous tissue
Palmar-plantar erythrodysaesthesia | 11% | 5%
Infections
Infection | 11% | 4%
Respiratory, thoracic and mediastinal
Epistaxis | 5% | 0%

Platinum-Sensitive Recurrent Epithelial Ovarian, Fallopian Tube, or Primary Peritoneal Cancer

Study AVF4095g

The safety of bevacizumab was evaluated in 247 patients who received at least one dose of bevacizumab in a double-blind study (AVF4095g) in patients with platinum sensitive recurrent epithelial ovarian, fallopian tube or primary peritoneal cancer [see Clinical Studies (14.9) ]. Patients were randomized (1:1) to receive bevacizumab (15 mg/kg) or placebo every 3 weeks with carboplatin and gemcitabine for 6 to 10 cycles followed by bevacizumab or placebo alone until disease progression or unacceptable toxicity. The demographics of the safety population were similar to the demographics of the efficacy population.

Grades 3-4 adverse reactions occurring at a higher incidence (≥ 2%) in patients receiving bevacizumab with chemotherapy compared to placebo with chemotherapy were: thrombocytopenia (40% vs. 34%), nausea (4% vs. 1.3%), fatigue (6% vs. 4%), headache (4% vs. 0.9%), proteinuria (10% vs. 0.4%), dyspnea (4% vs. 1.7%), epistaxis (5% vs. 0.4%), and hypertension (17% vs. 0.9%). Adverse reactions are presented in Table 7.

Table 7: Grades 1-5 Adverse Reactions Occurring at a Higher Incidence (≥ 5%) in Patients Receiving Bevacizumab with Chemotherapy vs. Placebo with Chemotherapy in Study AVF4095g
Adverse Reaction [NCI-CTC version 3] | Bevacizumab with Carboplatin and Gemcitabine; (N = 247) | Placebo with Carboplatin and Gemcitabine; (N = 233)
General
Fatigue | 82% | 75%
Mucosal inflammation | 15% | 10%
Gastrointestinal
Nausea | 72% | 66%
Diarrhea | 38% | 29%
Stomatitis | 15% | 7%
Hemorrhoids | 8% | 3%
Gingival bleeding | 7% | 0%
Hematology
Thrombocytopenia | 58% | 51%
Respiratory, thoracic and mediastinal
Epistaxis | 55% | 14%
Dyspnea | 30% | 24%
Cough | 26% | 18%
Oropharyngeal pain | 16% | 10%
Dysphonia | 13% | 3%
Rhinorrhea | 10% | 4%
Sinus congestion | 8% | 2%
Nervous system
Headache | 49% | 30%
Dizziness | 23% | 17%
Vascular
Hypertension | 42% | 9%
Musculoskeletal and connective tissue
Arthralgia | 28% | 19%
Back pain | 21% | 13%
Psychiatric
Insomnia | 21% | 15%
Renal and urinary
Proteinuria | 20% | 3%
Injury and procedural
Contusion | 17% | 9%
Infections
Sinusitis | 15% | 9%

Study GOG-0213

The safety of bevacizumab was evaluated in an open-label, controlled study (GOG-0213) in 325 patients with platinum-sensitive recurrent epithelial ovarian, fallopian tube, or primary peritoneal cancer, who have not received more than one previous regimen of chemotherapy [see Clinical Studies (14.9)]. Patients were randomized (1:1) to receive carboplatin and paclitaxel for 6 to 8 cycles or bevacizumab (15 mg/kg every 3 weeks) with carboplatin and paclitaxel for 6 to 8 cycles followed by bevacizumab as a single agent until disease progression or unacceptable toxicity. The demographics of the safety population were similar to the demographics of the efficacy population.

Grades 3-4 adverse reactions occurring at a higher incidence (≥ 2%) in patients receiving bevacizumab with chemotherapy compared to chemotherapy alone were: hypertension (11% vs. 0.6%), fatigue (8% vs. 3%), febrile neutropenia (6% vs. 3%), proteinuria (8% vs. 0%), abdominal pain (6% vs. 0.9%), hyponatremia (4% vs. 0.9%), headache (3% vs. 0.9%), and pain in extremity (3% vs. 0%). Adverse reactions are presented in Table 8.

Table 8: Grades1-5 Adverse Reactions Occurring at Higher Incidence (≥ 5) in Patients Receiving Bevacizumab with Chemotherapy vs. Chemotherapy Alone in Study GOG-0213
Adverse Reaction [NCI-CTC version 3] | Bevacizumab with Carboplatin and Paclitaxel; (N = 325) | Carboplatin and Paclitaxel; (N = 332)
Musculoskeletal and connective tissue
Arthralgia | 45% | 30%
Myalgia | 29% | 18%
Pain in extremity | 25% | 14%
Back pain | 17% | 10%
Muscular weakness | 13% | 8%
Neck pain | 9% | 0%
Vascular
Hypertension | 42% | 3%
Gastrointestinal
Diarrhea | 39% | 32%
Abdominal pain | 33% | 28%
Vomiting | 33% | 25%
Stomatitis | 33% | 16%
Nervous System
Headache | 38% | 20%
Dysarthria | 14% | 2%
Dizziness | 13% | 8%
Metabolism and nutrition
Decreased appetite | 35% | 25%
Hyperglycemia | 31% | 24%
Hypomagnesemia | 27% | 17%
Hyponatremia | 17% | 6%
Weight loss | 15% | 4%
Hypocalcemia | 12% | 5%
Hypoalbuminemia | 11% | 6%
Hyperkalemia | 9% | 3%
Respiratory, thoracic and mediastinal
Epistaxis | 33% | 2%
Dyspnea | 30% | 25%
Cough | 30% | 17%
Rhinitis allergic | 17% | 4%
Nasal mucosal disorder | 14% | 3%
Skin and subcutaneous tissue
Exfoliative rash | 23% | 16%
Nail disorder | 10% | 2%
Dry skin | 7% | 2%
Renal and urinary
Proteinuria | 17% | 1%
Increased blood creatinine | 13% | 5%
Hepatic
Increased aspartate aminotransferase | 15% | 9%
General
Chest pain | 8% | 2%
Infections
Sinusitis | 7% | 2%

6.2 Immunogenicity

The observed incidence of anti-drug antibodies is highly dependent on the sensitivity and specificity of the assay. Differences in assay methods preclude meaningful comparisons of the incidence of anti-drug antibodies in the studies described below with the incidence of anti-drug antibodies in other studies, including those of bevacizumab or of other bevacizumab products.

In clinical studies for adjuvant treatment of a solid tumor, 0.6% (14/2233) of patients tested positive for treatment-emergent anti-bevacizumab antibodies as detected by an electrochemiluminescent (ECL) based assay. Among these 14 patients, three tested positive for neutralizing antibodies against bevacizumab using an enzyme-linked immunosorbent assay (ELISA). The clinical significance of these anti-bevacizumab antibodies is not known.

6.3 Postmarketing Experience

The following adverse reactions have been identified during postapproval use of bevacizumab products. Because these reactions are reported voluntarily from a population of uncertain size, it is not always possible to reliably estimate their frequency or establish a causal relationship to drug exposure.

General: Polyserositis

Cardiovascular: Pulmonary hypertension, Mesenteric venous occlusion

Gastrointestinal: Gastrointestinal ulcer, Intestinal necrosis, Anastomotic ulceration

Hemic and lymphatic: Pancytopenia

Hepatobiliary disorders: Gallbladder perforation

Musculoskeletal and Connective Tissue Disorders: Osteonecrosis of the jaw

Renal: Renal thrombotic microangiopathy (manifested as severe proteinuria)

Respiratory: Nasal septum perforation

Vascular: Arterial (including aortic) aneurysms, dissections, and rupture

7 DRUG INTERACTIONS

Effects of Jobevne on Other Drugs

No clinically meaningful effect on the pharmacokinetics of irinotecan or its active metabolite SN38, interferon alfa, carboplatin or paclitaxel was observed when bevacizumab was administered in combination with these drugs; however, 3 of the 8 patients receiving bevacizumab with paclitaxel and carboplatin had lower paclitaxel exposure after four cycles of treatment (at Day 63) than those at Day 0, while patients receiving paclitaxel and carboplatin alone had a greater paclitaxel exposure at Day 63 than at Day 0.

8 USE IN SPECIFIC POPULATIONS

8.1 Pregnancy

Risk Summary

Based on findings from animal studies and their mechanism of action [see Clinical Pharmacology (12.1)], bevacizumab products may cause fetal harm in pregnant women. Limited postmarketing reports describe cases of fetal malformations with use of bevacizumab products in pregnancy; however, these reports are insufficient to determine drug-associated risks. In animal reproduction studies, intravenous administration of bevacizumab to pregnant rabbits every 3 days during organogenesis at doses approximately 1 to 10 times the clinical dose of 10 mg/kg produced fetal resorptions, decreased maternal and fetal weight gain and multiple congenital malformations including corneal opacities and abnormal ossification of the skull and skeleton including limb and phalangeal defects (see Data). Furthermore, animal models link angiogenesis and VEGF and VEGFR2 to critical aspects of female reproduction, embryo-fetal development, and postnatal development. Advise pregnant women of the potential risk to a fetus.

In the U.S. general population, the estimated background risk of major birth defects and miscarriage in clinically recognized pregnancies is 2% to 4% and 15% to 20%, respectively.

Data

Animal Data

Pregnant rabbits dosed with 10 mg/kg to 100 mg/kg bevacizumab (approximately 1 to 10 times the clinical dose of 10 mg/kg) every three days during the period of organogenesis (gestation day 6−18) exhibited decreases in maternal and fetal body weights and increased number of fetal resorptions. There were dose-related increases in the number of litters containing fetuses with any type of malformation (42% for the 0 mg/kg dose, 76% for the 30 mg/kg dose, and 95% for the 100 mg/kg dose) or fetal alterations (9% for the 0 mg/kg dose, 15% for the 30 mg/kg dose, and 61% for the 100 mg/kg dose). Skeletal deformities were observed at all dose levels, with some abnormalities including meningocele observed only at the 100 mg/kg dose level. Teratogenic effects included: reduced or irregular ossification in the skull, jaw, spine, ribs, tibia and bones of the paws; fontanel, rib and hindlimb deformities; corneal opacity; and absent hindlimb phalanges.

8.2 Lactation

Risk Summary

No data are available regarding the presence of bevacizumab products in human milk, the effects on the breast fed infant, or the effects on milk production. Human IgG is present in human milk, but published data suggest that breast milk antibodies do not enter the neonatal and infant circulation in substantial amounts. Because of the potential for serious adverse reactions in breastfed infants, advise women not to breastfeed during treatment with Jobevne and for 6 months after the last dose.

8.3 Females and Males of Reproductive Potential

Contraception

Females

Bevacizumab products may cause fetal harm when administered to a pregnant woman [see Use in Specific Populations (8.1)]. Advise females of reproductive potential to use effective contraception during treatment with Jobevne and for 6 months after the last dose.

Infertility

Females

Bevacizumab products increase the risk of ovarian failure and may impair fertility. Inform females of reproductive potential of the risk of ovarian failure prior to the first-dose of Jobevne. Long-term effects of bevacizumab products on fertility are not known.

In a clinical study of 179 premenopausal women randomized to receive chemotherapy with or without bevacizumab, the incidence of ovarian failure was higher in patients who received bevacizumab with chemotherapy (34%) compared to patients who received chemotherapy alone (2%). After discontinuing bevacizumab with chemotherapy, recovery of ovarian function occurred in 22% of these patients [see Warnings and Precautions (5.11), Adverse Reactions (6.1)].

8.4 Pediatric Use

The safety and effectiveness of Jobevne in pediatric patients have not been established.

In published literature reports, cases of non-mandibular osteonecrosis have been observed in patients under the age of 18 years who received bevacizumab. Bevacizumab products are not approved for use in patients under the age of 18 years.

Antitumor activity was not observed among eight pediatric patients with relapsed GBM who received bevacizumab and irinotecan. Addition of bevacizumab to standard of care did not result in improved event-free survival in pediatric patients enrolled in two randomized clinical studies, one in high grade glioma (n = 121) and one in metastatic rhabdomyosarcoma or non-rhabdomyosarcoma soft tissue sarcoma (n = 154).

Based on the population pharmacokinetics analysis of data from 152 pediatric and young adult patients with cancer (7 months to 21 years of age), bevacizumab clearance normalized by body weight in pediatrics was comparable to that in adults.

Juvenile Animal Toxicity Data

Juvenile cynomolgus monkeys with open growth plates exhibited physeal dysplasia following 4 to 26 weeks exposure at 0.4 to 20 times the recommended human dose (based on mg/kg and exposure). The incidence and severity of physeal dysplasia were dose-related and were partially reversible upon cessation of treatment.

8.5 Geriatric Use

In an exploratory pooled analysis of 1745 patients from five randomized, controlled studies, 35% of patients were ≥ 65 years old. The overall incidence of ATE was increased in all patients receiving bevacizumab with chemotherapy as compared to those receiving chemotherapy alone, regardless of age; however, the increase in the incidence of ATE was greater in patients ≥ 65 years (8% vs. 3%) as compared to patients < 65 years (2% vs. 1%) [see Warnings and Precautions (5.4)].

11 DESCRIPTION

Bevacizumab-nwgd is a vascular endothelial growth factor inhibitor. Bevacizumab-nwgd is a recombinant humanized monoclonal IgG1 antibody that contains human framework regions and murine complementarity-determining regions. Bevacizumab-nwgd has an approximate molecular weight of 149 kDa. Bevacizumab-nwgd is produced in a mammalian cell (Chinese Hamster Ovary) expression system.

Jobevne (bevacizumab-nwgd) injection is a sterile, preservative-free, clear to slightly opalescent, colorless to pale brown solution in a single-dose vial for intravenous use. Jobevne contains bevacizumab-nwgd at a concentration of 25 mg/mL in either a 100 mg/4 mL or 400 mg/16 mL single-dose vial.

Each mL of solution contains 25 mg bevacizumab-nwgd, dibasic sodium phosphate (1.2 mg), monobasic sodium phosphate (4.5 mg), polysorbate 20 (0.4 mg), trehalose (54.3 mg) and Water for Injection, USP. Sodium hydroxide and phosphoric acid may be used to adjust pH to 6.2 during manufacturing.

12 CLINICAL PHARMACOLOGY

12.1 Mechanism of Action

Bevacizumab products bind VEGF and prevent the interaction of VEGF to its receptors (Flt-1 and KDR) on the surface of endothelial cells. The interaction of VEGF with its receptors leads to endothelial cell proliferation and new blood vessel formation in in vitro models of angiogenesis. Administration of bevacizumab to xenotransplant models of colon cancer in nude (athymic) mice caused reduction of microvascular growth and inhibition of metastatic disease progression.

12.3 Pharmacokinetics

The pharmacokinetic profile of bevacizumab was assessed using an assay that measures total serum bevacizumab concentrations (i.e., the assay did not distinguish between free bevacizumab and bevacizumab bound to VEGF ligand). Based on a population pharmacokinetic analysis of 491 patients who received 1 to 20 mg/kg of bevacizumab every week, every 2 weeks, or every 3 weeks, bevacizumab pharmacokinetics are linear and the predicted time to reach more than 90% of steady state concentration is 84 days. The accumulation ratio following a dose of 10 mg/kg of bevacizumab once every 2 weeks is 2.8.

Population simulations of bevacizumab exposures provide a median trough concentration of 80.3 mcg/mL on Day 84 (10th, 90th percentile: 45, 128) following a dose of 5 mg/kg once every two weeks.

Distribution

The mean (% coefficient of variation [CV%]) central volume of distribution is 2.9 (22%) L.

Elimination

The mean (CV%) clearance is 0.23 (33) L/day. The estimated half-life is 20 days (11 to 50 days).

Specific Populations

The clearance of bevacizumab varied by body weight, sex, and tumor burden. After correcting for body weight, males had a higher bevacizumab clearance (0.26 L/day vs. 0.21 L/day) and a larger central volume of distribution (3.2 L vs. 2.7 L) than females. Patients with higher tumor burden (at or above median value of tumor surface area) had a higher bevacizumab clearance (0.25 L/day vs. 0.20 L/day) than patients with tumor burdens below the median. In Study AVF2107g, there was no evidence of lesser efficacy (hazard ratio for overall survival) in males or patients with higher tumor burden treated with bevacizumab as compared to females and patients with low tumor burden.

13 NONCLINICAL TOXICOLOGY

13.1 Carcinogenesis, Mutagenesis, Impairment of Fertility

No studies have been conducted to assess potential of bevacizumab products for carcinogenicity or mutagenicity.

Bevacizumab products may impair fertility. Female cynomolgus monkeys treated with 0.4 to 20 times the recommended human dose of bevacizumab exhibited arrested follicular development or absent corpora lutea, as well as dose-related decreases in ovarian and uterine weights, endometrial proliferation, and the number of menstrual cycles. Following a 4- or 12-week recovery period, there was a trend suggestive of reversibility. After the 12-week recovery period, follicular maturation arrest was no longer observed, but ovarian weights were still moderately decreased. Reduced endometrial proliferation was no longer observed at the 12-week recovery time point; however, decreased uterine weight, absent corpora lutea, and reduced number of menstrual cycles remained evident.

13.2 Animal Toxicology and/or Pharmacology

Rabbits dosed with bevacizumab exhibited reduced wound healing capacity. Using full-thickness skin incision and partial thickness circular dermal wound models, bevacizumab dosing resulted in reductions in wound tensile strength, decreased granulation and re-epithelialization, and delayed time to wound closure.

14 CLINICAL STUDIES

14.1 Metastatic Colorectal Cancer

Study AVF2107g

The safety and efficacy of bevacizumab was evaluated in a double-blind, active-controlled study [AVF2107g (NCT00109070)] in 923 patients with previously untreated mCRC who were randomized (1:1:1) to placebo with bolus-IFL (irinotecan 125 mg/m^2, fluorouracil 500 mg/m^2, and leucovorin 20 mg/m^2 given once weekly for 4 weeks every 6 weeks), bevacizumab (5 mg/kg every 2 weeks) with bolus-IFL, or bevacizumab (5 mg/kg every 2 weeks) with fluorouracil and leucovorin. Enrollment to the bevacizumab with fluorouracil and leucovorin arm was discontinued after enrollment of 110 patients in accordance with the protocol-specified adaptive design. Bevacizumab was continued until disease progression or unacceptable toxicity or for a maximum of 96 weeks. The main outcome measure was overall survival (OS).

The median age was 60 years; 60% were male, 79% were White, 57% had an ECOG performance status of 0, 21% had a rectal primary and 28% received prior adjuvant chemotherapy. The dominant site of disease was extra-abdominal in 56% of patients and was the liver in 38% of patients.

The addition of bevacizumab improved survival across subgroups defined by age (< 65 years, ≥ 65 years) and sex. Results are presented in Table 9 and Figure 1.

Table 9: Efficacy Results in Study AVF2107g
Efficacy Parameter | Bevacizumab with bolus-IFL; (N = 402) | Placebo with bolus-IFL; (N = 411)
Overall Survival
Median, in months | 20.3 | 15.6
Hazard ratio; (95% CI) | 0.66; (0.54, 0.81)
p-value [by stratified log-rank test.] | < 0.001
Progression-Free Survival
Median, in months | 10.6 | 6.2
Hazard ratio; (95% CI) | 0.54; (0.45, 0.66)
p-value | < 0.001
Overall Response Rate
Rate (%) | 45% | 35%
p-value [by χ^2 test.] | < 0.01
Duration of Response
Median, in months | 10.4 | 7.1

Figure 1: Kaplan-Meier Curves for Duration of Survival in Metastatic Colorectal Cancer in Study AVF2107g

Among the 110 patients randomized to bevacizumab with fluorouracil and leucovorin, median OS was 18.3 months, median progression-free survival (PFS) was 8.8 months, overall response rate (ORR) was 39%, and median duration of response was 8.5 months.

Study E3200

The safety and efficacy of bevacizumab were evaluated in a randomized, open-label, active-controlled study [E3200 (NCT00025337)] in 829 patients who were previously treated with irinotecan and fluorouracil for initial therapy for metastatic disease or as adjuvant therapy. Patients were randomized (1:1:1) to FOLFOX4 (Day 1: oxaliplatin 85 mg/m^2 and leucovorin 200 mg/m^2 concurrently, then fluorouracil 400 mg/m^2 bolus followed by 600 mg/m^2 continuously; Day 2: leucovorin 200 mg/m^2, then fluorouracil 400 mg/m^2 bolus followed by 600 mg/m^2 continuously; every 2 weeks), bevacizumab (10 mg/kg every 2 weeks prior to FOLFOX4 on Day 1) with FOLFOX4, or bevacizumab alone (10 mg/kg every 2 weeks). Bevacizumab was continued until disease progression or unacceptable toxicity. The main outcome measure was OS.

The bevacizumab alone arm was closed to accrual after enrollment of 244 of the planned 290 patients following a planned interim analysis by the data monitoring committee based on evidence of decreased survival compared to FOLFOX4 alone.

The median age was 61 years; 60% were male, 87% were White, 49% had an ECOG performance status of 0, 26% received prior radiation therapy, and 80% received prior adjuvant chemotherapy, 99% received prior irinotecan with or without fluorouracil for metastatic disease, and 1% received prior irinotecan and fluorouracil as adjuvant therapy.

The addition of bevacizumab to FOLFOX4 resulted in significantly longer survival as compared to FOLFOX4 alone; median OS was 13.0 months vs. 10.8 months [hazard ratio (HR) 0.75 (95% CI: 0.63, 0.89), p-value of 0.001 stratified log-rank test] with clinical benefit seen in subgroups defined by age (< 65 years, ≥ 65 years) and sex. PFS and ORR based on investigator assessment were higher in patients receiving bevacizumab with FOLFOX4.

Study TRC-0301

The activity of bevacizumab with fluorouracil (as bolus or infusion) and leucovorin was evaluated in a single arm study [TRC-0301 (NCT00066846)] enrolling 339 patients with mCRC with disease progression following both irinotecan-and oxaliplatin-based chemotherapy. Seventy-three percent of patients received concurrent bolus fluorouracil and leucovorin. One objective partial response was verified in the first 100 evaluable patients for an ORR of 1% (95% CI: 0%, 5.5%).

Study ML18147

The safety and efficacy of bevacizumab were evaluated in a prospective, randomized, open-label, multinational, controlled study [ML18147 (NCT00700102)] in 820 patients with histologically confirmed mCRC who had progressed on a first-line bevacizumab-containing regimen. Patients were excluded if they progressed within 3 months of initiating first-line chemotherapy and if they received bevacizumab for less than 3 consecutive months in the first-line setting. Patients were randomized (1:1) within 3 months after discontinuing bevacizumab as first-line treatment to receive fluoropyrimidine-irinotecan-or fluoropyrimidine-oxaliplatin-based chemotherapy with or without bevacizumab (5 mg/kg every 2 weeks or 7.5 mg/kg every 3 weeks). The choice of second-line treatment was contingent upon first-line chemotherapy. Second-line treatment was administered until progressive disease or unacceptable toxicity. The main outcome measure was OS. A secondary outcome measure was ORR.

The median age was 63 years (21 to 84 years); 64% were male, 52% had an ECOG performance status of 1, 44% had an ECOG performance status of 0, 58% received irinotecan-based therapy as first-line treatment, 55% progressed on first-line treatment within 9 months, and 77% received their last dose of bevacizumab as first-line treatment within 42 days of being randomized. Second-line chemotherapy regimens were generally balanced between each arm.

The addition of bevacizumab to fluoropyrimidine-based chemotherapy resulted in a statistically significant prolongation of OS and PFS. There was no significant difference in ORR. Results are presented in Table 10 and Figure 2.

Table 10: Efficacy Results in Study ML18147
Efficacy Parameter | Bevacizumab with Chemotherapy; (N = 409) | Chemotherapy; (N = 411)
Overall Survival [p = 0.0057 by unstratified log-rank test.]
Median, in months | 11.2 | 9.8
Hazard ratio (95% CI) | 0.81 (0.69, 0.94)
Progression-Free Survival [p-value < 0.0001 by unstratified log-rank test.]
Median, in months | 5.7 | 4.0
Hazard ratio (95% CI) | 0.68 (0.59, 0.78)

Figure 2: Kaplan-Meier Curves for Duration of Survival in Metastatic Colorectal Cancer in Study ML18147

14.2 Lack of Efficacy in Adjuvant Treatment of Colon Cancer

Lack of efficacy of bevacizumab as an adjunct to standard chemotherapy for the adjuvant treatment of colon cancer was determined in two randomized, open-label, multicenter clinical studies. The first study [BO17920 (NCT00112918)] was conducted in 3451 patients with high-risk stage II and III colon cancer, who had undergone surgery for colon cancer with curative intent. Patients were randomized to receive bevacizumab at a dose equivalent to 2.5 mg/kg/week on either a 2-weekly schedule with FOLFOX4 (N = 1155) or on a 3-weekly schedule with XELOX (N = 1145) or FOLFOX4 alone (N = 1151). The main outcome measure was disease free survival (DFS) in patients with stage III colon cancer.

The median age was 58 years; 54% were male, 84% were White and 29% were ≥ 65 years. Eighty-three percent had stage III disease.

The addition of bevacizumab to chemotherapy did not improve DFS. As compared to FOLFOX4 alone, the proportion of stage III patients with disease recurrence or with death due to disease progression were numerically higher for patients receiving bevacizumab with FOLFOX4 or with XELOX. The hazard ratios for DFS were 1.17 (95% CI: 0.98,1.39) for bevacizumab with FOLFOX4 versus FOLFOX4 alone and 1.07 (95% CI: 0.90, 1.28) for bevacizumab with XELOX versus FOLFOX4 alone. The hazard ratios for OS were 1.31 (95% CI: 1.03, 1.67) and 1.27 (95% CI: 1, 1.62) for the comparison of bevacizumab with FOLFOX4 versus FOLFOX4 alone and bevacizumab with XELOX versus FOLFOX4 alone, respectively. Similar lack of efficacy for DFS was observed in the bevacizumab-containing arms compared to FOLFOX4 alone in the high-risk stage II cohort.

In a second study [NSABP-C-08 (NCT00096278)], patients with stage II and III colon cancer who had undergone surgery with curative intent, were randomized to receive either bevacizumab administered at a dose equivalent to 2.5 mg/kg/week with mFOLFOX6 (N = 1354) or mFOLFOX6 alone (N = 1356). The median age was 57 years, 50% were male and 87% White. Seventy-five percent had stage III disease. The main outcome was DFS among stage III patients. The HR for DFS was 0.92 (95% CI: 0.77, 1.10). OS was not significantly improved with the addition of bevacizumab to mFOLFOX6 [HR 0.96 (95% CI: 0.75,1.22)].

14.3 First-Line Non–Squamous Non–Small Cell Lung Cancer

Study E4599

The safety and efficacy of bevacizumab as first-line treatment of patients with locally advanced, metastatic, or recurrent non–squamous NSCLC was studied in a single, large, randomized, active-controlled, open-label, multicenter study [E4599 (NCT00021060)]. A total of 878 chemotherapy-naïve patients with locally advanced, metastatic or recurrent non–squamous NSCLC were randomized (1:1) to receive six 21-day cycles of paclitaxel (200 mg/m^2) and carboplatin (AUC 6) with or without bevacizumab 15 mg/kg. After completing or discontinuing chemotherapy, patients randomized to receive bevacizumab continued to receive bevacizumab alone until disease progression or until unacceptable toxicity. The trial excluded patients with predominant squamous histology (mixed cell type tumors only), CNS metastasis, gross hemoptysis (1/2 teaspoon or more of red blood), unstable angina, or receiving therapeutic anticoagulation. The main outcome measure was duration of survival.

The median age was 63 years; 54% were male, 43% were ≥ 65 years, and 28% had ≥ 5% weight loss at study entry. Eleven percent had recurrent disease. Of the 89% with newly diagnosed NSCLC, 12% had Stage IIIB with malignant pleural effusion and 76% had Stage IV disease.

OS was statistically significantly longer for patients receiving bevacizumab with paclitaxel and carboplatin compared with those receiving chemotherapy alone. Median OS was 12.3 months vs. 10.3 months [HR 0.80 (95% CI: 0.68, 0.94), final p-value of 0.013, stratified log-rank test]. Based on investigator assessment which was not independently verified, patients were reported to have longer PFS with bevacizumab with paclitaxel and carboplatin compared to chemotherapy alone. Results are presented in Figure 3.

Figure 3: Kaplan-Meier Curves for Duration of Survival in First-Line Non-Squamous Non-Small Cell Lung Cancer in Study E4599

In an exploratory analysis across patient subgroups, the impact of bevacizumab on OS was less robust in the following subgroups: women [HR 0.99 (95% CI: 0.79, 1.25)], patients ≥ 65 years [HR 0.91 (95% CI: 0.72, 1.14)] and patients with ≥ 5% weight loss at study entry [HR 0.96 (95% CI: 0.73, 1.26)].

Study BO17704

The safety and efficacy of bevacizumab in patients with locally advanced, metastatic or recurrent non-squamous NSCLC, who had not received prior chemotherapy was studied in another randomized, double-blind, placebo-controlled study [BO17704 (NCT00806923)]. A total of 1043 patients were randomized (1:1:1) to receive cisplatin and gemcitabine with placebo, bevacizumab 7.5 mg/kg or bevacizumab 15 mg/kg. The main outcome measure was PFS. Secondary outcome measure was OS.

The median age was 58 years; 36% were female and 29% were ≥ 65 years. Eight percent had recurrent disease and 77% had Stage IV disease.

PFS was significantly higher in both bevacizumab-containing arms compared to the placebo arm [HR 0.75 (95% CI: 0.62, 0.91), p-value of 0.0026 for bevacizumab 7.5 mg/kg and HR 0.82 (95% CI: 0.68; 0.98), p-value of 0.0301 for bevacizumab 15 mg/kg]. The addition of bevacizumab to cisplatin and gemcitabine failed to demonstrate an improvement in the duration of OS [HR 0.93 (95% CI: 0.78; 1.11), p-value of 0.420 for bevacizumab 7.5 mg/kg and HR 1.03 (95% CI: 0.86, 1.23), p-value of 0.761 for bevacizumab 15 mg/kg].

14.4 Recurrent Glioblastoma

Study EORTC 26101

The safety and efficacy of bevacizumab were evaluated in a multicenter, randomized (2:1), open-label study in patients with recurrent GBM (EORTC 26101, NCT01290939). Patients with first progression following radiotherapy and temozolomide were randomized (2:1) to receive bevacizumab (10 mg/kg every 2 weeks) with lomustine (90 mg/m^2 every 6 weeks) or lomustine (110 mg/m^2 every 6 weeks) alone until disease progression or unacceptable toxicity. Randomization was stratified by World Health Organization performance status (0 vs. > 0), steroid use (yes vs. no), largest tumor diameter (≤ 40 vs. > 40 mm), and institution. The main outcome measure was OS. Secondary outcome measures were investigator-assessed PFS and ORR per the modified Response Assessment in Neuro-oncology (RANO) criteria, health related quality of life (HRQoL), cognitive function, and corticosteroid use.

A total of 432 patients were randomized to receive lomustine alone (N = 149) or bevacizumab with lomustine (N = 283). The median age was 57 years; 24.8% of patients were ≥ 65 years. The majority of patients with were male (61%); 66% had a WHO performance status score > 0; and in 56% the largest tumor diameter was ≤ 40 mm. Approximately 33% of patients randomized to receive lomustine received bevacizumab following documented progression.

No difference in OS (HR 0.91, p -value of 0.4578) was observed between arms; therefore, all secondary outcome measures are descriptive only. PFS was longer in the bevacizumab with lomustine arm [HR 0.52 (95% CI: 0.41, 0.64)] with a median PFS of 4.2 months in the bevacizumab with lomustine arm and 1.5 months in the lomustine arm. Among the 50% of patients receiving corticosteroids at the time of randomization, a higher percentage of patients in the bevacizumab with lomustine arm discontinued corticosteroids (23% vs. 12%).

Study AVF3708g and Study NCI 06-C-0064E

The efficacy and safety of bevacizumab 10 mg/kg every 2 weeks in patients with previously treated GBM were evaluated in one single arm single center study (NCI 06-C-0064E) and a randomized noncomparative multicenter study [AVF3708g (NCT00345163)]. Response rates in both studies were evaluated based on modified WHO criteria that considered corticosteroid use. In AVF3708g, the response rate was 25.9% (95% CI: 17%, 36.1%) with a median duration of response of 4.2 months (95% CI: 3, 5.7). In Study NCI 06-C-0064E, the response rate was 19.6% (95% CI: 10.9%, 31.3%) with a median duration of response of 3.9 months (95% CI: 2.4, 17.4).

14.5 Metastatic Renal Cell Carcinoma

Study BO17705

The safety and efficacy of bevacizumab were evaluated in patients with treatment-naïve mRCC in a multicenter, randomized, double-blind, international study [BO17705 (NCT00738530)] comparing interferon alfa and bevacizumab versus interferon alfa and placebo. A total of 649 patients who had undergone a nephrectomy were randomized (1:1) to receive either bevacizumab (10 mg/kg every 2 weeks; N = 327) or placebo (every 2 weeks; N = 322) with interferon alfa (9 MIU subcutaneously three times weekly for a maximum of 52 weeks). Patients were treated until disease progression or unacceptable toxicity. The main outcome measure was investigator-assessed PFS. Secondary outcome measures were ORR and OS.

The median age was 60 years (18 to 82 years); 70% were male and 96% were White. The study population was characterized by Motzer scores as follows: 28% favorable (0), 56% intermediate (1-2), 8% poor (3−5), and 7% missing.

PFS was statistically significantly prolonged among patients receiving bevacizumab compared to placebo; median PFS was 10.2 months vs. 5.4 months [HR 0.60 (95% CI: 0.49, 0.72), p-value < 0.0001, stratified log-rank test]. Among the 595 patients with measurable disease, ORR was also significantly higher (30% vs. 12%, p-value < 0.0001, stratified CMH test). There was no improvement in OS based on the final analysis conducted after 444 deaths, with a median OS of 23 months in the patients receiving bevacizumab with interferon alfa and 21 months in patients receiving interferon alone [HR 0.86, (95% CI: 0.72, 1.04)]. Results are presented in Figure 4.

Figure 4: Kaplan-Meier Curves for Progression-Free Survival in Metastatic Renal Cell Carcinoma in Study BO17705

14.6 Persistent, Recurrent, or Metastatic Cervical Cancer

Study GOG-0240

The safety and efficacy of bevacizumab were evaluated in patients with persistent, recurrent, or metastatic cervical cancer in a randomized, four-arm, multicenter study comparing bevacizumab with chemotherapy versus chemotherapy alone [GOG-0240 (NCT00803062)]. A total of 452 patients were randomized (1:1:1:1) to receive paclitaxel and cisplatin with or without bevacizumab, or paclitaxel and topotecan with or without bevacizumab.

The dosing regimens for bevacizumab, paclitaxel, cisplatin and topotecan were as follows:

- Day 1: Paclitaxel 135 mg/m^2 over 24 hours, Day 2: cisplatin 50 mg/m^2 with bevacizumab;
- Day 1: Paclitaxel 175 mg/m^2 over 3 hours, Day 2: cisplatin 50 mg/m^2 with bevacizumab;
- Day 1: Paclitaxel 175 mg/m^2 over 3 hours with cisplatin 50 mg/m^2 with bevacizumab;
- Day 1: Paclitaxel 175 mg/m^2 over 3 hours with bevacizumab, Days 1-3: topotecan IV 0.75 mg/m^2 over 30 minutes

Patients were treated until disease progression or unacceptable adverse reactions. The main outcome measure was OS. Secondary outcome measures included ORR.

The median age was 48 years (20 to 85 years). Of the 452 patients randomized at baseline, 78% of patients were White, 80% had received prior radiation, 74% had received prior chemotherapy concurrent with radiation, and 32% had a platinum-free interval of less than 6 months. Patients had a GOG performance status of 0 (58%) or 1 (42%). Demographic and disease characteristics were balanced across arms.

Results are presented in Figure 5 and Table 11.

Figure 5: Kaplan-Meier Curves for Overall Survival in Persistent, Recurrent, or Metastatic Cervical Cancer in Study GOG-0240

Table 11: Efficacy Results in Study GOG-0240
Efficacy Parameter | Bevacizumab with Chemotherapy; (N = 227) | Chemotherapy; (N = 225)
Overall Survival
Median, in months [Kaplan-Meier estimates.] | 16.8 | 12.9
Hazard ratio (95% CI) | 0.74 (0.58, 0.94)
p-value [log-rank test (stratified).] | 0.0132

The ORR was higher in patients who received bevacizumab with chemotherapy [45% (95% CI: 39, 52)] compared to patients who received chemotherapy alone [34% (95% CI: 28,40)].

Table 12: Efficacy Results in Study GOG-0240
Efficacy Parameter | Topotecan and; Paclitaxel with or; without Bevacizumab; (N = 223) | Cisplatin and Paclitaxel; with or without Bevacizumab; (N = 229)
Overall Survival
Median, in months [Kaplan-Meier estimates.] | 13.3 | 15.5
Hazard ratio (95% CI) | 1.15 (0.91, 1.46)
p-value | 0.23

The HR for OS with bevacizumab with cisplatin and paclitaxel as compared to cisplatin and paclitaxel alone was 0.72 (95% CI: 0.51,1.02). The HR for OS with bevacizumab with topotecan and paclitaxel as compared to topotecan and paclitaxel alone was 0.76 (95% CI: 0.55, 1.06).

14.7 Stage III or IV Epithelial Ovarian, Fallopian Tube, or Primary Peritoneal Cancer Following Initial Surgical Resection

Study GOG-0218

The safety and efficacy of bevacizumab were evaluated in a multicenter, randomized, double-blind, placebo controlled, three arm study [Study GOG-0218 (NCT00262847)] evaluating the effect of adding bevacizumab to carboplatin and paclitaxel for the treatment of patients with stage III or IV epithelial ovarian, fallopian tube or primary peritoneal cancer (N=1873) following initial surgical resection. Patients were randomized (1:1:1) to one of the following arms:

- CPP: carboplatin (AUC 6) and paclitaxel (175 mg/m^2) for six cycles, with concurrent placebo started at cycle 2, followed by placebo alone every three weeks for a total of up to 22 cycles of therapy (n=625) or
- CPB15: carboplatin (AUC 6) and paclitaxel (175 mg/m^2) for six cycles, with concurrent bevacizumab started at cycle 2, followed by placebo alone every three weeks for a total of up to 22 cycles of therapy (n = 625) or
- CPB15+: carboplatin (AUC 6) and paclitaxel (175 mg/m^2) for six cycles, with concurrent bevacizumab started at cycle 2, followed by bevacizumab as a single agent every three weeks for a total of up to 22 cycles of therapy (n = 623).

The main outcome measure was investigator-assessed PFS. OS was a secondary outcome measure.

The median age was 60 years (range 22-89 years) and 28% of patients were > 65 years of age. Overall, approximately 50% of patients had a GOG PS of 0 at baseline, and 43% a GOG PS score of 1. Patients had either epithelial ovarian cancer (83%), primary peritoneal cancer (15%), or fallopian tube cancer (2%). Serous adenocarcinoma was the most common histologic type (85% in CPP and CPB15 arms, 86% in CPB15+ arm). Overall, approximately 34% of patients had resected FIGO Stage III with residual disease < 1 cm, 40% had resected Stage III with residual disease > 1 cm, and 26% had resected Stage IV disease.

The majority of patients in all three treatment arms received subsequent antineoplastic treatment, 78.1% in the CPP arm, 78.6% in the CPB15 arm, and 73.2% in the CPB15+ arm. A higher proportion of patients in the CPP arm (25.3%) and CPB15 arm (26.6%) received at least one anti-angiogenic (including bevacizumab) treatment after discontinuing from study compared with the CPB15+ arm (15.6%).

Study results are presented in Table 13 and Figure 6.

Table 13: Efficacy Results in Study GOG-0218
Efficacy Parameter | Bevacizumab with carboplatin and paclitaxel followed by bevacizumab alone; (N = 623) | Bevacizumab with carboplatin and paclitaxel; (N = 625) | Carboplatin and paclitaxel; (N = 625)
Progression-Free Survival per Investigator
Median, in months | 18.2 | 12.8 | 12.0
Hazard ratio (95% CI) [Relative to the control arm; stratified hazard ratio] | 0.62 (0.52, 0.75) | 0.83 (0.70, 0.98)
p-value [Two-sided p-value based on re-randomization test] | < 0.0001 | NS
Overall Survival [Final overall survival analysis]
Median, in months | 43.8 | 38.8 | 40.6
Hazard ratio (95% CI) | 0.89 (0.76, 1.05) | 1.06 (0.90, 1.24)
NS=not significant

Figure 6: Kaplan-Meier Curves for Investigator-Assessed Progression-Free Survival in Stage III or IV Epithelial Ovarian, Fallopian Tube, or Primary Peritoneal Cancer Following Initial Surgical Resection in Study GOG-0218

14.8 Platinum-Resistant Recurrent Epithelial Ovarian, Fallopian Tube, or Primary Peritoneal Cancer

Study MO22224

The safety and efficacy of bevacizumab were evaluated in a multicenter, open-label, randomized study [MO22224 (NCT00976911)] comparing bevacizumab with chemotherapy versus chemotherapy alone in patients with platinum-resistant, recurrent epithelial ovarian, fallopian tube, or primary peritoneal cancer that recurred within < 6 months from the most recent platinum-based therapy (N = 361). Patients had received no more than 2 prior chemotherapy regimens. Patients received one of the following chemotherapy regimens at the discretion of the investigator: paclitaxel (80 mg/m^2 on days 1, 8, 15 and 22 every 4 weeks; pegylated liposomal doxorubicin 40 mg/m^2 on day 1 every 4 weeks; or topotecan 4 mg/m^2 on days 1, 8 and 15 every 4 weeks or 1.25 mg/m^2 on days 1-5 every 3 weeks). Patients were treated until disease progression, unacceptable toxicity, or withdrawal. Forty percent of patients on the chemotherapy alone arm received bevacizumab alone upon progression. The main outcome measure was investigator-assessed PFS. Secondary outcome measures were ORR and OS.

The median age was 61 years (25 to 84 years) and 37% of patients were ≥ 65 years. Seventy-nine percent had measurable disease at baseline, 87% had baseline CA-125 levels ≥ 2 times ULN and 31% had ascites at baseline. Seventy-three percent had a PFI of 3 months to 6 months and 27% had PFI of < 3 months. ECOG performance status was 0 for 59%, 1 for 34% and 2 for 7% of the patients.

The addition of bevacizumab to chemotherapy demonstrated a statistically significant improvement in investigator-assessed PFS, which was supported by a retrospective independent review analysis. Results for the ITT population are presented in Table 14 and Figure 7. Results for the separate chemotherapy cohorts are presented in Table 15.

Table 14: Efficacy Results in Study MO22224
Efficacy Parameter | Bevacizumab with Chemotherapy; (N = 179) | Chemotherapy; (N = 182)
Progression-Free Survival per Investigator
Median (95% CI), in months | 6.8 (5.6, 7.8) | 3.4 (2.1, 3.8)
HR (95% CI) [per stratified Cox proportional hazards model.] | 0.38 (0.30, 0.49)
p-value [per stratified log-rank test.] | < 0.0001
Overall Survival
Median (95% CI), in months | 16.6 (13.7, 19.0) | 13.3 (11.9, 16.4)
HR (95% CI) | 0.89 (0.69, 1.14)
Overall Response Rate
Number of Patients with Measurable Disease at Baseline | 142 | 144
Rate, % (95% CI) | 28% (21%, 36%) | 13% (7%, 18%)
Duration of Response
Median, in months | 9.4 | 5.4

Figure 7: Kaplan-Meier Curves for Investigator-Assessed Progression-Free Survival in Platinum-Resistant Recurrent Epithelial Ovarian, Fallopian Tube, or Primary Peritoneal Cancer in Study MO22224

Table 15: Efficacy Results in Study MO22224 by Chemotherapy
Efficacy Parameter | Paclitaxel |  | Topotecan |  | Pegylated Liposomal Doxorubicin
Efficacy Parameter | Bevacizumab with Chemotherapy; (N = 60) | Chemotherapy; (N = 55) | Bevacizumab with Chemotherapy; (N = 57) | Chemotherapy; (N = 63) | Bevacizumab with Chemotherapy; (N = 62) | Chemotherapy; (N = 64)
Progression-Free Survival per Investigator
Median, in months; (95% CI) | 9.6; (7.8, 11.5) | 3.9; (3.5, 5.5) | 6.2; (5.3, 7.6) | 2.1; (1.9, 2.3) | 5.1; (3.9, 6.3) | 3.5; (1.9, 3.9)
Hazard ratio [per stratified Cox proportional hazards model.]; (95% CI) | 0.47; (0.31, 0.72) |  | 0.24; (0.15, 0.38) |  | 0.47; (0.32, 0.71)
Overall Survival
Median, in months; (95% CI) | 22.4; (16.7, 26.7) | 13.2; (8.2, 19.7) | 13.8; (11.0, 18.3) | 13.3; (10.4, 18.3) | 13.7; (11.0, 18.3) | 14.1; (9.9, 17.8)
Hazard ratio (95% CI) | 0.64; (0.41, 1.01) |  | 1.12; (0.73, 1.73) |  | 0.94; (0.63, 1.42)
Overall Response Rate
Number of patients with measurable disease at baseline | 45 | 43 | 46 | 50 | 51 | 51
Rate, %; (95% CI) | 53; (39, 68) | 30; (17, 44) | 17; (6, 28) | 2; (0, 6) | 16; (6, 26) | 8; (0, 15)
Duration of Response
Median, in months | 11.6 | 6.8 | 5.2 | NE | 8.0 | 4.6
NE = Not Estimable

14.9 Platinum-Sensitive Recurrent Epithelial Ovarian, Fallopian Tube, or Primary Peritoneal Cancer

Study AVF4095g

The safety and efficacy of bevacizumab were evaluated in a randomized, double-blind, placebo-controlled study [AVF4095g (NCT00434642)] studying bevacizumab with chemotherapy versus chemotherapy alone in the treatment of patients with platinum-sensitive recurrent epithelial ovarian, fallopian tube, or primary peritoneal cancer who have not received prior chemotherapy in the recurrent setting or prior bevacizumab treatment (N = 484). Patients were randomized (1:1) to receive bevacizumab (15 mg/kg day 1) or placebo every 3 weeks with carboplatin (AUC 4, day 1) and gemcitabine (1000 mg/m^2 on days 1 and 8) a for 6 to 10 cycles followed by bevacizumab or placebo alone until disease progression or unacceptable toxicity. The main outcome measures were investigator-assessed PFS. Secondary outcome measures were ORR and OS.

The median age was 61 years (28 to 87 years) and 37% of patients were ≥ 65 years. All patients had measurable disease at baseline, 74% had baseline CA-125 levels >ULN (35 U/mL). The PFI was 6 months to 12 months in 42 % of patients and >12 months in 58% of patients. The ECOG performance status was 0 or 1 for 99.8% of patients.

A statistically significant prolongation in PFS was demonstrated among patients receiving bevacizumab with chemotherapy compared to those receiving placebo with chemotherapy (Table 16 and Figure 8). Independent radiology review of PFS was consistent with investigator assessment [HR 0.45 (95% CI: 0.35, 0.58)]. OS was not significantly improved with the addition of bevacizumab to chemotherapy [HR 0.95 (95% CI: 0.77, 1.17)].

Table 16: Efficacy Results in Study AVF4095g
Efficacy Parameter | Bevacizumab with Gemcitabine and Carboplatin; (N = 242) | Placebo with Gemcitabine and Carboplatin; (N =242)
Progression-Free Survival
Median, in months | 12.4 | 8.4
Hazard ratio; (95% CI) | 0.46; 0.37, 0.58)
p-value | < 0.0001
Overall Response Rate
% patients with overall response | 78% | 57%
p-value | < 0.0001

Figure 8: Kaplan Meier Curves for Progression-Free Survival in Platinum-Sensitive Recurrent Epithelial Ovarian, Fallopian Tube, or Primary Peritoneal Cancer in Study AVF4095g

Study GOG-0213

The safety and efficacy of bevacizumab were evaluated in a randomized, controlled, open-label study [Study GOG0213 (NCT00565851)] of bevacizumab with chemotherapy versus chemotherapy alone in the treatment of patients with platinum-sensitive recurrent epithelial ovarian, fallopian tube, or primary peritoneal cancer, who have not received more than one previous regimen of chemotherapy (N = 673). Patients were randomized (1:1) to receive carboplatin (AUC 5) and paclitaxel (175 mg/m^2 IV over 3 hours) every 3 weeks for 6 to 8 cycles (N=336) or bevacizumab (15 mg/kg) every 3 weeks with carboplatin (AUC 5) and paclitaxel (175 mg/m^2 IV over 3 hours) for 6 to 8 cycles followed by bevacizumab (15 mg/kg every 3 weeks) as a single agent until disease progression or unacceptable toxicity. The main outcome measure was OS. Other outcome measures were investigator-assessed PFS, and ORR.

The median age was 60 years (23 to 85 years) and 33% of patients were ≥ 65 years. Eighty-three percent had measurable disease at baseline and 74% had abnormal CA-125 levels at baseline. Ten percent of patients had received prior bevacizumab. Twenty-six percent had a PFI of 6 months to 12 months and 74% had a PFI of >12 months. GOG performance status was 0 or 1 for 99% of patients.

Results are presented in Table 17 and Figure 9.

Table 17: Efficacy Results in Study GOG-0213
Efficacy Parameter | Bevacizumab with Carboplatin and Paclitaxel; (N = 337) | Carboplatin and Paclitaxel; (N = 336)
Overall Survival
Median, in months | 42.6 | 37.3
Hazard ratio (95% CI) (IVRS) [HR was estimated from Cox proportional hazards models stratified by the duration of treatment-free interval prior to enrolling onto this study per IVRS (interactive voice response system) and secondary surgical debulking status.] | 0.84 (0.69, 1.01)
Hazard ratio (95% CI) (eCRF) [HR was estimated from Cox proportional hazards models stratified by the duration of platinum free-interval prior to enrolling onto this study per eCRF (electronic case report form) and secondary surgical debulking status.] | 0.82 (0.68, 0.996)
Progression-Free Survival
Median, in months | 13.8 | 10.4
Hazard ratio (95% CI) (IVRS) | 0.61 (0.51, 0.72)
Overall Response Rate
Number of patients with measurable disease at baseline | 274 | 286
Rate, % | 213 (78%) | 159 (56%)

Figure 9: Kaplan Meier Curves for Overall Survival in Platinum-Sensitive Recurrent Epithelial Ovarian, Fallopian Tube, or Primary Peritoneal Cancer in Study GOG-0213

16 HOW SUPPLIED/STORAGE AND HANDLING

Jobevne (bevacizumab-nwgd) injection is a clear to slightly opalescent, colorless to pale brown, sterile solution for intravenous infusion supplied as single-dose vials in the following strengths:

- 100 mg/4 mL (25 mg/mL): carton of one vial (NDC 83257-009-11).
- 400 mg/16 mL (25 mg/mL): carton of one vial (NDC 83257-010-11).

Store refrigerated at 2°C to 8°C (36°F to 46°F) in the original carton until time of use to protect from light. Do not freeze or shake the vial or carton.

17 PATIENT COUNSELING INFORMATION

Gastrointestinal Perforations and Fistulae: Bevacizumab products may increase the risk of developing gastrointestinal perforations and fistulae. Advise patients to immediately contact their health care provider for high fever, rigors, persistent or severe abdominal pain, severe constipation, or vomiting [see Warnings and Precautions (5.1)].

Surgery and Wound Healing Complications: Bevacizumab products can increase the risk of wound healing complications. Instruct patients not to undergo surgery without first discussing this potential risk with their health care provider [see Warnings and Precautions (5.2)].

Hemorrhage: Bevacizumab products can increase the risk of hemorrhage. Advise patients to immediately contact their health care provider for signs and symptoms of serious or unusual bleeding including coughing or spitting blood [see Warnings and Precautions (5.3)].

Arterial and Venous Thromboembolic Events: Bevacizumab products increase the risk of arterial and venous thromboembolic events. Advise patients to immediately contact their health care provider for signs and symptoms of arterial or venous thromboembolism [see Warnings and Precautions (5.4, 5.5)].

Hypertension: Bevacizumab products can increase blood pressure. Advise patients that they will undergo routine blood pressure monitoring and to contact their health care provider if they experience changes in blood pressure [see Warnings and Precautions (5.6)].

Posterior Reversible Leukoencephalopathy Syndrome: Posterior reversible encephalopathy syndrome (PRES) has been associated with bevacizumab products treatment. Advise patients to immediately contact their health care provider for new onset or worsening neurological function [see Warnings and Precautions (5.7)].

Renal Injury and Proteinuria: Bevacizumab products increase the risk of proteinuria and renal injury, including nephrotic syndrome. Advise patients that treatment with Jobevne requires regular monitoring of renal function and to contact their health care provider for proteinuria or signs and symptoms of nephrotic syndrome [see Warnings and Precautions (5.8)].

Infusion-Related Reactions: Bevacizumab products can cause infusion-related reactions. Advise patients to contact their health care provider immediately for signs or symptoms of infusion-related reactions [see Warnings and Precautions (5.9)].

Congestive Heart Failure: Bevacizumab products can increase the risk of developing congestive heart failure. Advise patients to contact their health care provider immediately for signs and symptoms of CHF [see Warnings and Precautions (5.12)].

Embryo-Fetal Toxicity: Advise female patients that bevacizumab products may cause fetal harm and to inform their health care provider with a known or suspected pregnancy [see Warnings and Precautions (5.10), Use in Specific Populations (8.1)]. Advise females of reproductive potential to use effective contraception during treatment with Jobevne and for 6 months after the last dose [see Use in Specific Populations (8.3)].

Ovarian Failure: Bevacizumab products may lead to ovarian failure. Advise patients of potential options for preservation of ova prior to starting treatment [see Warnings and Precautions (5.11)].

Lactation: Advise women not to breastfeed during treatment with Jobevne and for 6 months after the last dose [see Use in Specific Populations (8.2)].

The brands listed are trademarks of their respective owners.

JOBEVNE™ is a trademark of Biosimilars Newco. Ltd.; a Biocon Biologics Company.

Copyright © 2025 Biocon Biologics Inc. All rights reserved.

Manufactured by:
Biocon Biologics Inc.
245 Main St, 2nd Floor
Cambridge, MA 02142, U.S.A.
U.S. License No. 2324

Product of India

Revised: 04/2025

KR/DRUGS/KTK/28D/07/2006

PRINCIPAL DISPLAY PANEL – 100 mg/4 mL

NDC 83257-009-11

Rx only

Jobevne™
(bevacizumab-nwgd)
Injection
100 mg/4 mL (25 mg/mL)

Must Be Diluted Before Intravenous Infusion

No preservative

1 Single-Dose
Vial

Discard Unused Portion

CONTENTS:
Each carton contains one preservative-free 100 mg (25 mg/mL) single-dose vial of Jobevne. Each mL of solution contains 25 mg bevacizumab-nwgd, dibasic sodium phosphate (1.2 mg), monobasic sodium phosphate (4.5 mg), polysorbate 20 (0.4 mg), trehalose (54.3 mg), and Water for Injection, USP. Sodium hydroxide and ortho phosphoric acid may be used to adjust pH to 6.2 during manufacturing.

Dosage: See prescribing information. Must be diluted before Intravenous Infusion.

STORAGE:
Refrigerate at 2°C to 8°C (36°F to 46°F).
Store in original carton to protect from light.

DO NOT FREEZE OR SHAKE.

JOBEVNE™ is a trademark of Biosimilars Newco. Ltd.; a Biocon Biologics Company.
Copyright © 2025 Biocon Biologics Inc. All rights reserved.

Manufactured by:
Biocon Biologics Inc.
245 Main St, 2nd Floor,
Cambridge, MA 02142, U.S.A
U.S. License No. 2324

Product of India

KR/DRUGS/KTK/28D/07/2006

PRINCIPAL DISPLAY PANEL – 400 mg/16 mL

NDC 83257-010-11

Rx only

Jobevne™
(bevacizumab-nwgd)
Injection
400 mg/16 mL (25 mg/mL)
Before Intravenous Infusion

Discard Unused Portion
No preservative

1 Single-Dose Vial

Must Be Diluted

CONTENTS:
Each carton contains one preservative-free 400 mg (25 mg/mL) single-dose vial of Jobevne. Each mL of solution contains 25 mg bevacizumab-nwgd, dibasic sodium phosphate (1.2 mg), monobasic sodium phosphate (4.5 mg), polysorbate 20 (0.4 mg), trehalose (54.3 mg), and Water for Injection, USP. Sodium hydroxide and ortho phosphoric acid may be used to adjust pH to 6.2 during manufacturing.

Dosage: See prescribing information. Must be diluted before Intravenous Infusion.

STORAGE:
Refrigerate at 2° to 8°C (36° to 46°F).
Store in original carton to protect from light.

DO NOT FREEZE OR SHAKE.

JOBEVNE™ is a trademark of Biosimilars Newco. Ltd.; a Biocon Biologics Company.
Copyright © 2025 Biocon Biologics Inc. All rights reserved.

Manufactured by:
Biocon Biologics Inc.
245 Main St, 2nd Floor
Cambridge, MA 02142, U.S.A.
U.S. License No. 2324

Product of India

KR/DRUGS/KTK/28D/07/2006